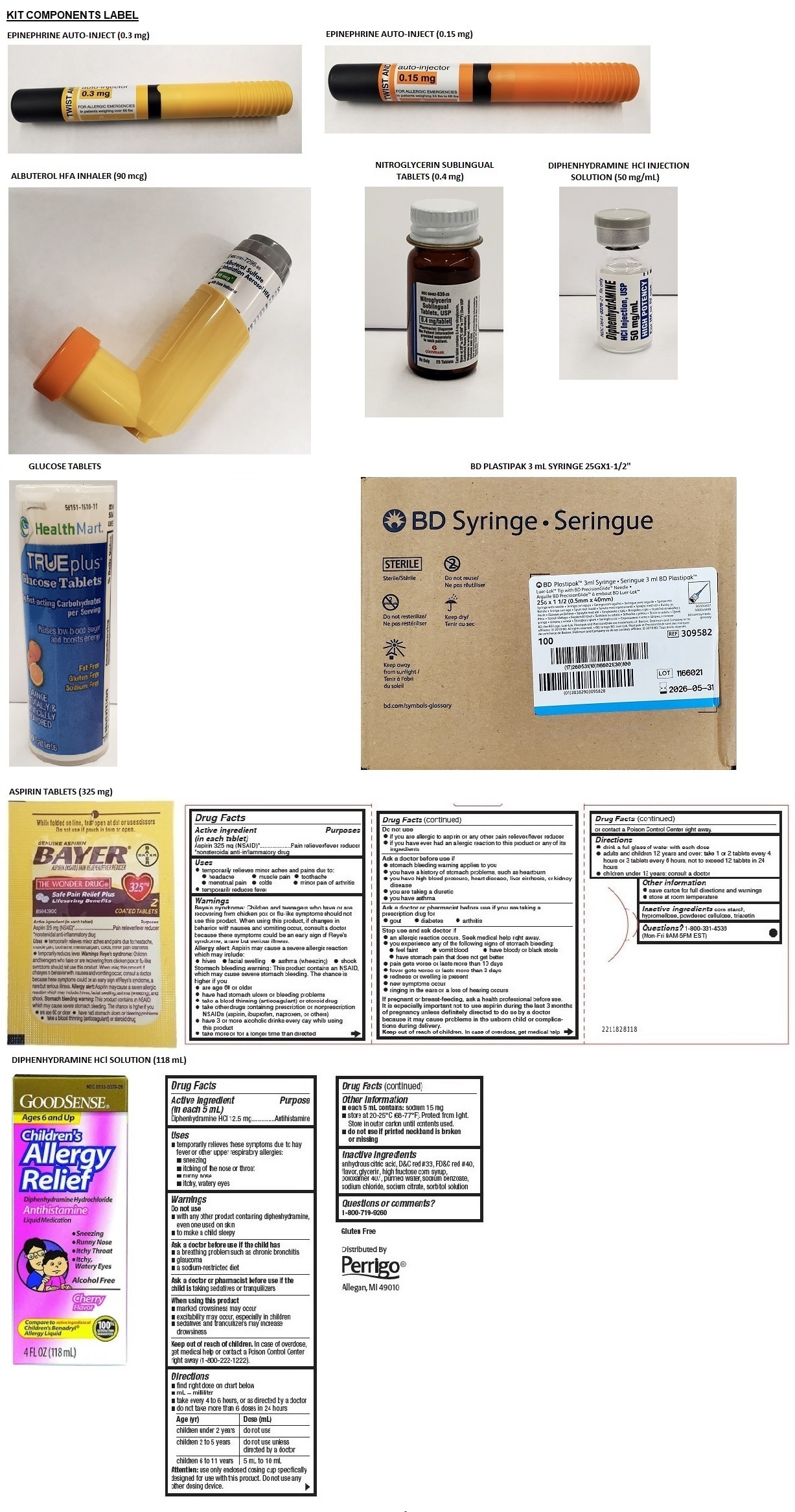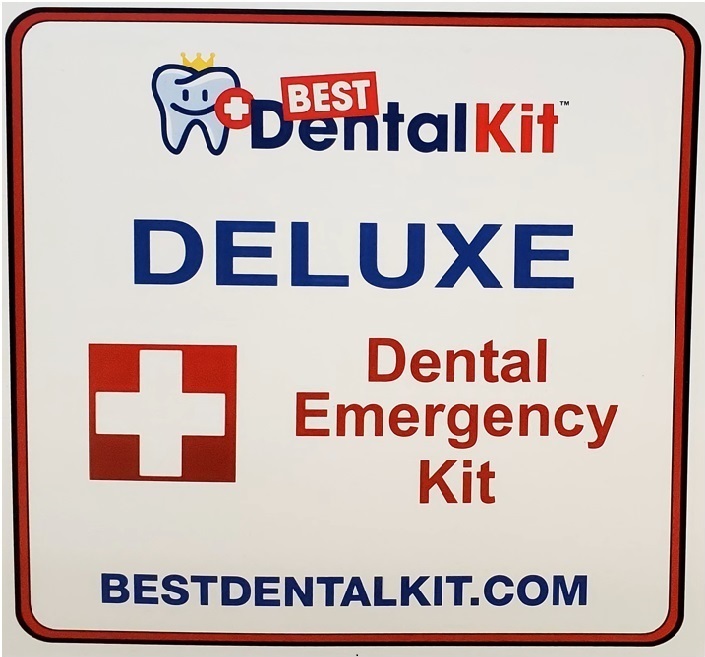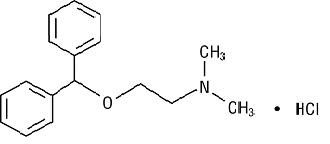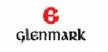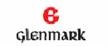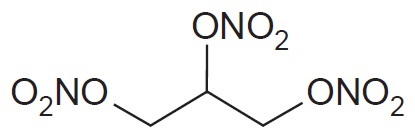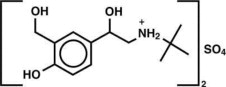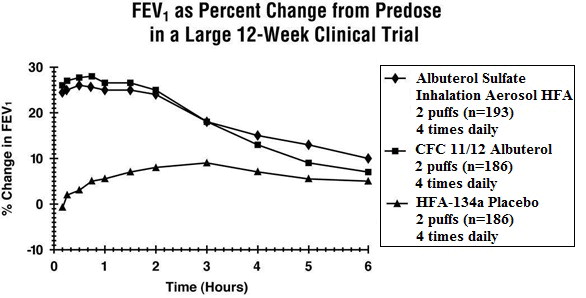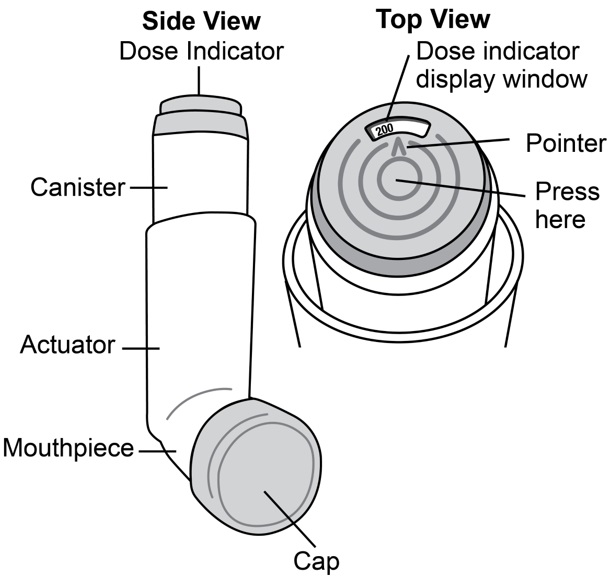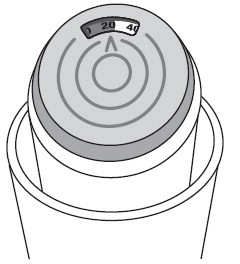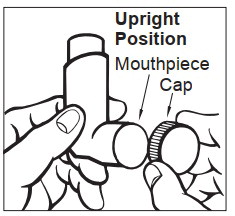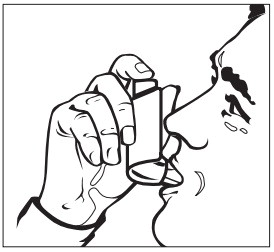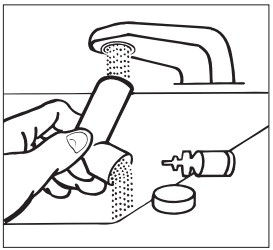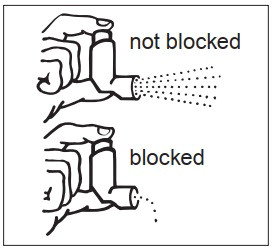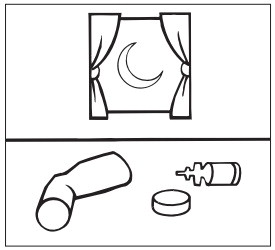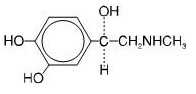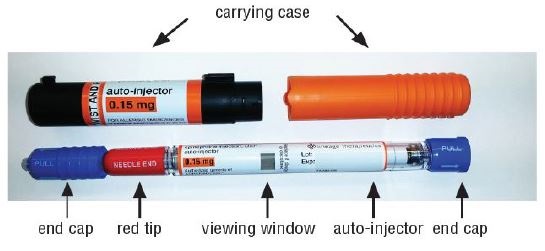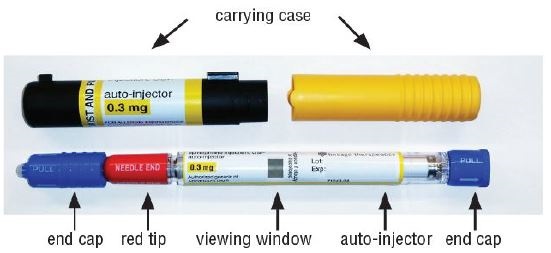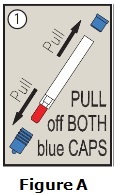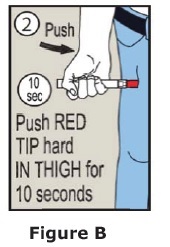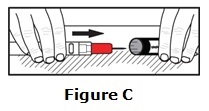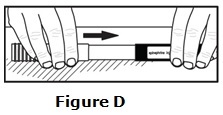 DRUG LABEL: Deluxe Dental Emergency Kit
NDC: 83220-001 | Form: KIT | Route: SUBCUTANEOUS
Manufacturer: Best Dental Kit LLC
Category: prescription | Type: HUMAN PRESCRIPTION DRUG LABEL
Date: 20251016

ACTIVE INGREDIENTS: EPINEPHRINE 0.3 mg/0.3 mL; EPINEPHRINE 0.15 mg/0.15 mL; ALBUTEROL SULFATE 108 ug/1 1; NITROGLYCERIN 0.4 mg/1 1; DIPHENHYDRAMINE HYDROCHLORIDE 50 mg/1 mL; ASPIRIN 325 mg/1 1; DIPHENHYDRAMINE HYDROCHLORIDE 12.5 mg/5 mL; ANHYDROUS DEXTROSE 4000 mg/1 1
INACTIVE INGREDIENTS: SODIUM CHLORIDE; CHLOROBUTANOL; SODIUM BISULFITE; HYDROCHLORIC ACID; SODIUM HYDROXIDE; SODIUM CHLORIDE; CHLOROBUTANOL; SODIUM BISULFITE; HYDROCHLORIC ACID; SODIUM HYDROXIDE; ALCOHOL; NORFLURANE; OLEIC ACID; CALCIUM STEARATE; CROSCARMELLOSE SODIUM; LACTOSE MONOHYDRATE; SILICA DIMETHYL SILYLATE; BENZETHONIUM CHLORIDE 100 ug/1 mL; WATER; SODIUM HYDROXIDE; HYDROCHLORIC ACID; CARNAUBA WAX; STARCH, CORN; HYPROMELLOSE, UNSPECIFIED; POWDERED CELLULOSE; TRIACETIN; ANHYDROUS CITRIC ACID; D&C RED NO. 33; FD&C RED NO. 40; GLYCERIN; HIGH FRUCTOSE CORN SYRUP; POLOXAMER 407; WATER; SODIUM BENZOATE; SODIUM CHLORIDE; SODIUM CITRATE, UNSPECIFIED FORM; SORBITOL; MALTODEXTRIN; CITRIC ACID MONOHYDRATE; MAGNESIUM STEARATE; MICROCRYSTALLINE CELLULOSE; ASCORBIC ACID; FD&C YELLOW NO. 6

HIGHLIGHTS OF PRESCRIBING INFORMATION

Deluxe Dental Emergency Kit
These highlights do not include all the information needed to use EPINEPHRINE INJECTION safely and effectively. See full prescribing information for EPINEPHRINE INJECTION.
EPINEPHRINE injection, for intramuscular or subcutaneous use
Initial U.S. Approval: 1939

1 INDICATIONS AND USAGE

Epinephrine injection is a non-selective alpha and beta-adrenergic receptor agonist, indicated in the emergency treatment of allergic reactions (Type I) including anaphylaxis.

2 DOSAGE AND ADMINISTRATION

- Patients greater than or equal to 30 kg (66 lbs): 0.3 mg (2)
- Patients 15 to 30 kg (33 lbs-66 lbs): 0.15 mg (2)

Inject intramuscularly or subcutaneously into the anterolateral aspect of the thigh, through clothing if necessary. Each device is a single-dose injection.

3 DOSAGE FORMS AND STRENGTHS

- Injection, 0.3 mg: 0.3 mg/0.3 mL epinephrine injection, USP, pre-filled auto-injector (3)
- Injection, 0.15 mg: 0.15 mg/0.15 mL epinephrine injection, USP, pre-filled auto-injector (3)

4 CONTRAINDICATIONS

None.

5 WARNINGS AND PRECAUTIONS

- In conjunction with use, seek immediate medical or hospital care. (5.1)
- Do not inject intravenously, into buttock, or into digits, hands, or feet. (5.2)
- To minimize the risk of injection related injury, hold the child’s leg firmly in place and limit movement prior to and during injection when administering to young children. (5.2)
- Rare cases of serious skin and soft tissue infections have been reported following epinephrine injection. Advise patients to seek medical care if they develop signs or symptoms of infection. (5.3)
- The presence of a sulfite in this product should not deter use. (5.4)
- Administer with caution in patients with heart disease; may aggravate angina pectoris or produce ventricular arrhythmias. (5.5)

6 ADVERSE REACTIONS

Adverse reactions to epinephrine include anxiety, apprehensiveness, restlessness, tremor, weakness, dizziness, sweating, palpitations, pallor, nausea and vomiting, headache, and/or respiratory difficulties.

To report SUSPECTED ADVERSE REACTIONS, contact Amneal Pharmaceuticals at 1-877-835-5472 or FDA at 1-800-FDA-1088 or www.fda.gov/medwatch.

7 DRUG INTERACTIONS

- Cardiac glycosides or diuretics: observe for development of cardiac arrhythmias. (7)
- Tricyclic antidepressants, monoamine oxidase inhibitors, levothyroxine sodium, and certain antihistamines: potentiate effects of epinephrine. (7)
- Beta-adrenergic blocking drugs: antagonize cardiostimulating and bronchodilating effects of epinephrine. (7)
- Alpha-adrenergic blocking drugs: antagonize vasoconstricting and hypertensive effects of epinephrine. (7)
- Ergot alkaloids: may reverse the pressor effects of epinephrine. (7)

8 USE IN SPECIFIC POPULATIONS

- Elderly patients may be at greater risk of developing adverse reactions. (5.5, 8.5)

1 INDICATIONS AND USAGE

Nitroglycerin sublingual tablets are nitrate vasodilator indicated for relief of an attack or prophylaxis of angina pectoris due to coronary artery disease. (1)

2 DOSAGE AND ADMINISTRATION

- At the onset of an attack, administer one tablet under the tongue or buccal pouch. One additional tablet may be administered every 5 minutes as needed. No more than 3 total tablets are recommended within a 15 minute period. (2)
- If chest pain persists after three tablets, seek prompt medical attention. (2)
- May be used prophylactically 5 to 10 minutes prior to engaging in activities that might precipitate an acute attack. (2)

3 DOSAGE FORMS AND STRENGTHS

Sublingual tablets, 0.3 mg; 0.4 mg; 0.6 mg (3)

4 CONTRAINDICATIONS

- Use of phosphodiesterase type 5 (PDE-5) inhibitors, such as avanafil, sildenafil, tadalafil, or vardenafil, or soluble guanylate cyclase (sGC) stimulators. (4.1, 7.1)
- Severe anemia (4.2)
- Increased intracranial pressure (4.3)
- Hypersensitivity to nitroglycerin sublingual tablets or to other nitrates or nitrites or any excipient (4.4)
- Circulatory failure and shock (4.5)

6 ADVERSE REACTIONS

Most common adverse reactions occurring at a frequency greater than 2% are headache, dizziness and paresthesia. (6)

To report SUSPECTED ADVERSE REACTIONS, contact Glenmark Pharmaceuticals Inc., USA at 1 (888) 721-7115 or FDA at 1-800-FDA-1088 or www.fda.gov/medwatch.

FULL PRESCRIBING INFORMATION

1 INDICATIONS AND USAGE

Epinephrine injection is indicated in the emergency treatment of allergic reactions (Type I) including anaphylaxis to stinging insects (e.g., order Hymenoptera, which includes bees, wasps, hornets, yellow jackets and fire ants), and biting insects (e.g., triatoma, mosquitoes), allergen immunotherapy, foods, drugs, diagnostic testing substances (e.g., radiocontrast media), and other allergens, as well as idiopathic anaphylaxis or exercise-induced anaphylaxis.

Epinephrine injection is intended for immediate administration in patients who are determined to be at increased risk for anaphylaxis, including individuals with a history of anaphylactic reactions.

Anaphylactic reactions may occur within minutes after exposure and consist of flushing, apprehension, syncope, tachycardia, thready or unobtainable pulse associated with a fall in blood pressure, convulsions, vomiting, diarrhea and abdominal cramps, involuntary voiding, wheezing, dyspnea due to laryngeal spasm, pruritus, rashes, urticaria, or angioedema.

Epinephrine injection is intended for immediate administration as emergency supportive therapy only and is not a replacement or substitute for immediate medical care.

2 DOSAGE AND ADMINISTRATION

2.1 Recommended Dosage According to Patient Body Weight

- Patients greater than or equal to 30 kg (approximately 66 pounds or more): 0.3 mg
- Patients 15 kg to 30 kg (33 pounds to 66 pounds): 0.15 mg

2.2 Administration Instructions

- Inject the single-dose epinephrine injection intramuscularly or subcutaneously into the anterolateral aspect of the thigh, through clothing if necessary. Do not inject intravenously, and do not inject into buttocks, into digits, hands or feet [see Warnings and Precautions (5.2)].
- Instruct caregivers of young children who are prescribed an epinephrine injection and who may be uncooperative and kick or move during an injection to hold the leg firmly in place and limit movement prior to and during an injection [see Warnings and Precautions (5.2)].
- Each epinephrine injection is a single-dose of epinephrine injection for single use. Since the doses of epinephrine delivered from epinephrine injection are fixed, consider using other forms of injectable epinephrine if doses lower than 0.15 mg are deemed necessary.
- With severe persistent anaphylaxis, repeat injections with an additional epinephrine injection may be necessary. More than two sequential doses of epinephrine should only be administered under direct medical supervision [see Warnings and Precautions (5.1)].
- The epinephrine solution in the viewing window of epinephrine injection should be inspected visually for particulate matter and discoloration.

3 DOSAGE FORMS AND STRENGTHS

- Injection: 0.3 mg (0.3 mg/0.3 mL) of clear and colorless solution in single-dose pre-filled auto-injector
- Injection: 0.15 mg (0.15 mg/0.15 mL) of clear and colorless solution in single-dose pre-filled auto-injector

4 CONTRAINDICATIONS

None.

5 WARNINGS AND PRECAUTIONS

5.1 Emergency Treatment

Epinephrine injection is intended for immediate administration as emergency supportive therapy and is not intended as a substitute for immediate medical care. In conjunction with the administration of epinephrine, the patient should seek immediate medical or hospital care. More than two sequential doses of epinephrine should only be administered under direct medical supervision [see Indications and Usage (1), Dosage and Administration (2) and Patient Counseling Information (17)].

5.2 Injection-Related Complications

Epinephrine injection should only be injected into the anterolateral aspect of the thigh [see Dosage and Administration (2) and Patient Counseling Information (17)].

Do not inject intravenously

Large doses or accidental intravenous injection of epinephrine may result in cerebral hemorrhage due to a sharp rise in blood pressure. Rapidly acting vasodilators can counteract the marked pressor effects of epinephrine if there is such inadvertent administration.

Do not inject into buttock

Injection into the buttock may not provide effective treatment of anaphylaxis. Advise the patient to go immediately to the nearest emergency room for further treatment of anaphylaxis. Additionally, injection into the buttock has been associated with the development of Clostridial infections (gas gangrene). Cleansing with alcohol does not kill bacterial spores, and therefore, does not lower the risk.

Do not inject into digits, hands or feet

Since epinephrine is a strong vasoconstrictor, accidental injection into the digits, hands or feet may result in loss of blood flow to the affected area. Advise the patient to go immediately to the nearest emergency room and to inform the healthcare provider in the emergency room of the location of the accidental injection. Treatment of such inadvertent administration should consist of vasodilation, in addition to further appropriate treatment of anaphylaxis [see Adverse Reactions (6)].

Hold leg firmly during injection

Lacerations, bent needles, and embedded needles have been reported when epinephrine has been injected into the thigh of young children who are uncooperative and kick or move during an injection. To minimize the risk of injection related injury when administering, hold the child’s leg firmly in place and limit movement prior to and during injection.

5.3 Serious Infections at the Injection Site

Rare cases of serious skin and soft tissue infections, including necrotizing fasciitis and myonecrosis caused by Clostridia (gas gangrene), have been reported at the injection site following epinephrine injection for anaphylaxis. Clostridium spores can be present on the skin and introduced into the deep tissue with subcutaneous or intramuscular injection. While cleansing with alcohol may reduce presence of bacteria on the skin, alcohol cleansing does not kill Clostridium spores. To decrease the risk of Clostridium infection, do not inject epinephrine injection into the buttock [see Warnings and Precautions (5.2)]. Advise patients to seek medical care if they develop signs or symptoms of infection, such as persistent redness, warmth, swelling, or tenderness, at the epinephrine injection site.

5.4 Allergic Reactions Associated with Sulfite

The presence of a sulfite in this product should not deter administration of the drug for treatment of serious allergic or other emergency situations even if the patient is sulfite-sensitive.

Epinephrine is the preferred treatment for serious allergic reactions or other emergency situations even though this product contains sodium bisulfite, a sulfite that may, in other products, cause allergic-type reactions including anaphylactic symptoms or life-threatening or less severe asthmatic episodes in certain susceptible persons.

The alternatives to using epinephrine in a life-threatening situation may not be satisfactory.

5.5 Disease Interactions

Some patients may be at greater risk for developing adverse reactions after epinephrine administration. Despite these concerns, it should be recognized that the presence of these conditions is not a contraindication to epinephrine administration in an acute, life-threatening situation. Therefore, patients with these conditions, and/or any other person who might be in a position to administer epinephrine injection to a patient experiencing anaphylaxis should be carefully instructed in regard to the circumstances under which epinephrine should be used.

Patients with Heart Disease

Epinephrine should be administered with caution to patients who have heart disease, including patients with cardiac arrhythmias, coronary artery or organic heart disease, or hypertension. In such patients, or in patients who are on drugs that may sensitize the heart to arrhythmias, epinephrine may precipitate or aggravate angina pectoris as well as produce ventricular arrhythmias [see Drug Interactions (7) and Adverse Reactions (6)].

Other Patients and Diseases

Epinephrine should be administered with caution to patients with hyperthyroidism, diabetes, elderly individuals, and pregnant women. Patients with Parkinson’s disease may notice a temporary worsening of symptoms.

6 ADVERSE REACTIONS

Due to the lack of randomized, controlled clinical trials of epinephrine for the treatment of anaphylaxis, the true incidence of adverse reactions associated with the systemic use of epinephrine is difficult to determine. Adverse reactions reported in observational trials, case reports, and studies are listed below.

Common adverse reactions to systemically administered epinephrine include anxiety; apprehensiveness; restlessness; tremor; weakness; dizziness; sweating; palpitations; pallor; nausea and vomiting; headache; and/or respiratory difficulties. These symptoms occur in some persons receiving therapeutic doses of epinephrine, but are more likely to occur in patients with hypertension or hyperthyroidism [see Warnings and Precautions (5.5)].

Cardiovascular Reactions

- Arrhythmias, including fatal ventricular fibrillation, have been reported, particularly in patients with underlying cardiac disease or those receiving certain drugs [see Warnings and Precautions (5.5) and Drug Interactions (7)].
- Rapid rises in blood pressure have produced cerebral hemorrhage, particularly in elderly patients with cardiovascular disease [see Warnings and Precautions (5.5)].
- Angina may occur in patients with coronary artery disease [see Warnings and Precautions (5.5)].
- Rare cases of stress cardiomyopathy have been reported in patients treated with epinephrine.

Reactions from Accidental Injection and/or Improper Technique

- Accidental injection into the digits, hands or feet may result in loss of blood flow to the affected area [see Warnings and Precautions (5.2)].
- Adverse reactions experienced as a result of accidental injections may include increased heart rate, local reactions including injection site pallor, coldness and hypoesthesia or injury at the injection site resulting in bruising, bleeding, discoloration, erythema or skeletal injury.
- Lacerations, bent needles, and embedded needles have been reported when epinephrine injection has been injected into the thigh of young children who are uncooperative and kick or move during an injection [see Warnings and Precautions (5.2)].
- Injection into the buttock has resulted in cases of gas gangrene [see Warnings and Precautions (5.2)].

Skin and Soft Tissue Infections

- Rare cases of serious skin and soft tissue infections, including necrotizing fasciitis and myonecrosis caused by Clostridia (gas gangrene), have been reported following epinephrine injection in the thigh [see Warnings and Precautions (5.3)].

7 DRUG INTERACTIONS

Cardiac Glycosides, Diuretics, and Anti-arrhythmics

Patients who receive epinephrine while concomitantly taking cardiac glycosides, diuretics, or anti-arrhythmics should be observed carefully for the development of cardiac arrhythmias [see Warnings and Precautions (5.5)].

Antidepressants, Monoamine Oxidase Inhibitors, Levothyroxine, and Antihistamines

The effects of epinephrine may be potentiated by tricyclic antidepressants, monoamine oxidase inhibitors, levothyroxine sodium, and certain antihistamines, notably chlorpheniramine, tripelennamine, and diphenhydramine.

Beta-Adrenergic Blockers

The cardiostimulating and bronchodilating effects of epinephrine are antagonized by beta- adrenergic blocking drugs, such as propranolol.

Alpha-Adrenergic Blockers

The vasoconstricting and hypertensive effects of epinephrine are antagonized by alpha-adrenergic blocking drugs, such as phentolamine.

Ergot Alkaloids

Ergot alkaloids may also reverse the pressor effects of epinephrine.

8 USE IN SPECIFIC POPULATIONS

8.1 Pregnancy

Risk Summary

There are no available human data on the use of epinephrine injection in pregnant women to inform a drug-associated risk of adverse developmental outcomes. In animal reproduction studies, epinephrine administered by the subcutaneous route to rabbits, mice, and hamsters during the period of organogenesis was teratogenic at doses 7 times and higher than the maximum recommended daily subcutaneous or intramuscular dose on a mg/m^2 basis (see Data). Epinephrine is the first-line medication of choice for the treatment of anaphylaxis during pregnancy in humans. Epinephrine should be used for treatment of anaphylaxis during pregnancy in the same manner as it is used in non-pregnant patients.

In the U.S. general population, the estimated background risk of major birth defects and miscarriage in clinically recognized pregnancies is 2 to 4% and 15 to 20%, respectively.

Clinical Considerations

Disease-associated maternal and embryo/fetal risk:

During pregnancy, anaphylaxis can be catastrophic and can lead to hypoxic-ischemic encephalopathy and permanent central nervous system damage or death in the mother and, more commonly, in the fetus or neonate. The prevalence of anaphylaxis occurring during pregnancy is reported to be approximately 3 cases per 100,000 deliveries.

Management of anaphylaxis during pregnancy is similar to management in the general population. Epinephrine is the first line-medication of choice for treatment of anaphylaxis; it should be used in the same manner in pregnant and non-pregnant patients. In conjunction with the administration of epinephrine, the patient should seek immediate medical or hospital care.

Data

Animal Data

In an embryofetal development study with rabbits dosed during the period of organogenesis, epinephrine was shown to be teratogenic (including gastroschisis and embryonic lethality) at doses approximately 40 times the maximum recommended intramuscular or subcutaneous dose (on a mg/m^2 basis at a maternal subcutaneous dose of 1.2 mg/kg/day for two to three days).

In an embryofetal development study with mice dosed during the period of organogenesis, epinephrine was shown to be teratogenic (including embryonic lethality) at doses approximately 8 times the maximum recommended intramuscular or subcutaneous dose (on a mg/m^2 basis at maternal subcutaneous dose of 1 mg/kg/day for 10 days). These effects were not seen in mice at approximately 4 times the maximum recommended daily intramuscular or subcutaneous dose (on a mg/m^2 basis at a subcutaneous maternal dose of 0.5 mg/kg/day for 10 days).

In an embryofetal development study with hamsters dosed during the period of organogenesis from gestation days 7 to 10, epinephrine was shown to be teratogenic at doses approximately 7 times the maximum recommended intramuscular or subcutaneous dose (on a mg/m^2 basis at a maternal subcutaneous dose of 0.5 mg/kg/day).

8.2 Lactation

Risk Summary

There are no data on the presence of epinephrine in human milk, or the effects of epinephrine on the breastfed infant or on milk production. Epinephrine is the first line-medication of choice for treatment of anaphylaxis; it should be used in the same manner in breastfeeding and no-breastfeeding patients.

8.4 Pediatric Use

Epinephrine injection may be administered to pediatric patients at a dosage appropriate to body weight [see Dosage and Administration (2.1)]. Clinical experience with the use of epinephrine suggests that the adverse reactions seen in children are similar in nature and extent to those both expected and reported in adults. Since the dose of epinephrine delivered from epinephrine injection is fixed, consider using other forms of injectable epinephrine if doses lower than 0.15 mg are deemed necessary.

8.5 Geriatric Use

Clinical studies for the treatment of anaphylaxis have not been performed in subjects aged 65 and over to determine whether they respond differently from younger subjects. However, other reported clinical experience with use of epinephrine for the treatment of anaphylaxis has identified that geriatric patients may be particularly sensitive to the effects of epinephrine. Therefore, epinephrine injection should be administered with caution in elderly individuals, who may be at greater risk for developing adverse reactions after epinephrine administration [see Warnings and Precautions (5.5) and Overdosage (10)].

10 OVERDOSAGE

Overdosage of epinephrine may produce extremely elevated arterial pressure, which may result in cerebrovascular hemorrhage, particularly in elderly patients. Overdosage may also result in pulmonary edema because of peripheral vascular constriction together with cardiac stimulation. Treatment consists of a rapidly acting vasodilators or alpha-adrenergic blocking drugs and/or respiratory support.

Epinephrine overdosage can also cause transient bradycardia followed by tachycardia, and these may be accompanied by potentially fatal cardiac arrhythmias. Premature ventricular contractions may appear within one minute after injection and may be followed by multifocal ventricular tachycardia (prefibrillation rhythm). Subsidence of the ventricular effects may be followed by atrial tachycardia and occasionally by atrioventricular block. Treatment of arrhythmias consists of administration of a beta-adrenergic blocking drug such as propranolol.

Overdosage sometimes results in extreme pallor and coldness of the skin, metabolic acidosis, and kidney failure. Suitable corrective measures must be taken in such situations.

11 DESCRIPTION

Epinephrine injection, USP 0.3 mg and 0.15 mg is an auto-injector and a combination product containing drug and device components.

Each epinephrine injection, USP 0.3 mg delivers a single dose of 0.3 mg epinephrine from epinephrine injection, USP (0.3 mL) in a sterile solution.

Each epinephrine injection, USP 0.15 mg delivers a single dose of 0.15 mg epinephrine from epinephrine injection, USP (0.15 mL) in a sterile solution.

Epinephrine injection, USP 0.3 mg and epinephrine injection, USP 0.15 mg each contain 1.1 mL of epinephrine solution. 0.3 mL and 0.15 mL epinephrine solution are dispensed for epinephrine injection, USP 0.3 mg and epinephrine injection, USP 0.15 mg, respectively, when activated. The solution remaining after activation is not available for future use and should be discarded.

Each 0.3 mL in epinephrine injection, USP 0.3 mg contains 0.3 mg epinephrine, 2.6 mg sodium chloride, not more than 1.5 mg chlorobutanol, 0.45 mg sodium bisulfite, hydrochloric acid and sodium hydroxide to adjust pH, and water for injection. The pH range is 2.2-5.0.

Each 0.15 mL in epinephrine injection, USP 0.15 mg contains 0.15 mg epinephrine, 1.3 mg sodium chloride, not more than 0.75 mg chlorobutanol, 0.225 sodium bisulfite, hydrochloric acid and sodium hydroxide to adjust pH, and water for injection. The pH range is 2.2-5.0.

Epinephrine is a sympathomimetic catecholamine. Chemically, epinephrine is (-)-3,4-Dihydroxy-α-[(methylamino)methyl]benzyl alcohol with the following structure:

Epinephrine solution deteriorates rapidly on exposure to air or light, turning pink from oxidation to adrenochrome and brown from the formation of melanin. Replace epinephrine injection, USP if the epinephrine solution appears discolored (pinkish or brown color), cloudy, or contains particles.

Thoroughly review the patient instructions and operation of epinephrine injection, USP with patients and caregivers prior to use [see Patient Counseling Information (17)].

12 CLINICAL PHARMACOLOGY

12.1 Mechanism of Action

Epinephrine acts on both alpha- and beta-adrenergic receptors.

12.2 Pharmacodynamics

Through its action on alpha-adrenergic receptors, epinephrine lessens the vasodilation and increased vascular permeability that occurs during anaphylaxis, which can lead to loss of intravascular fluid volume and hypotension.

Through its action on beta-adrenergic receptors, epinephrine causes bronchial smooth muscle relaxation and helps alleviate bronchospasm, wheezing, and dyspnea that may occur during anaphylaxis.

Epinephrine also alleviates pruritus, urticaria, and angioedema, and may relieve gastrointestinal and genitourinary symptoms associated with anaphylaxis because of its relaxer effects on the smooth muscle of the stomach, intestine, uterus and urinary bladder.

When given intramuscularly or subcutaneously, epinephrine has a rapid onset and short duration of action.

13 NONCLINICAL TOXICOLOGY

13.1 Carcinogenesis, Mutagenesis, Impairment of Fertility

Long-term studies to evaluate the carcinogenic potential of epinephrine have not been conducted.

Epinephrine and other catecholamines have been shown to have mutagenic potential in vitro. Epinephrine was positive in the Salmonella bacterial reverse mutation assay, positive in the mouse lymphoma assay, and negative in the in vivo micronucleus assay. Epinephrine is an oxidative mutagen based on the E. coli WP2 Mutoxitest bacterial reverse mutation assay. This should not prevent the use of epinephrine where indicated under the conditions noted under [see Indications and Usage (1)].

The potential for epinephrine to impair reproductive performance has not been evaluated, but epinephrine has been shown to decrease implantation in female rabbits dosed subcutaneously with 1.2 mg/kg/day (40-fold the highest human intramuscular or subcutaneous daily dose) during gestation days 3 to 9.

16 HOW SUPPLIED/STORAGE AND HANDLING

Storage and Handling

Protect from light. Epinephrine is light sensitive and should be stored in the carrying-case provided to protect it from light. Store at room temperature (20°C to 25°C (68°F to 77°F)); excursions permitted to 15°C to 30°C (59°F to 86°F) [See USP Controlled Room Temperature]. Do not refrigerate. Before using, check to make sure the solution in the auto-injector is clear and colorless. Replace the auto-injector if the solution is discolored (pinkish or brown color), cloudy, or contains particles.

Properly dispose of all used, unwanted, or expired epinephrine injection, USP.

17 PATIENT COUNSELING INFORMATION

See FDA-Approved Patient Labeling (Patient Information and Instructions for Use)

A healthcare provider should review the patient instructions and operation of epinephrine injection, in detail, with the patient or caregiver.

Epinephrine is essential for the treatment of anaphylaxis. Carefully instruct patients who are at risk of or with a history of severe allergic reactions (anaphylaxis) to insect stings or bites, foods, drugs, and other allergens, as well as idiopathic and exercise-induced anaphylaxis, about the circumstances under which epinephrine should be used.

Administration

Instruct patients and/or caregivers in the appropriate use of epinephrine injection. Epinephrine injection should be injected into the middle of the outer thigh (through clothing if necessary).

Instruct caregivers to hold the leg of young children firmly in place and limit movement prior to and during injection. Lacerations, bent needles, and embedded needles have been reported when epinephrine injection has been injected into the thigh of young children who are uncooperative and kick during an injection [see Warnings and Precautions (5.2)].

Advise patients to seek immediate medical care in conjunction with administration of epinephrine injection.

Complete patient information, including dosage, directions for proper administration and precautions can be found inside each epinephrine injection carton. A printed label on the surface of epinephrine injection shows instructions for use and a diagram depicting the injection process.

Training

Instruct patients and/or caregivers to use the Trainer to familiarize themselves with the use of epinephrine injection in an allergic emergency. The Trainer may be used multiple times.

Adverse Reactions

Epinephrine may produce symptoms and signs that include an increase in heart rate, the sensation of a more forceful heartbeat, palpitations, sweating, nausea and vomiting, difficulty breathing, pallor, dizziness, weakness or shakiness, headache, apprehension, nervousness, or anxiety. These signs and symptoms usually subside rapidly, especially with rest, quiet, and recumbency. Patients with hypertension or hyperthyroidism may develop more severe or persistent effects, and patients with coronary artery disease could experience angina. Patients with diabetes may develop increased blood glucose levels following epinephrine administration. Patients with Parkinson’s disease may notice a temporary worsening of symptoms [see Warnings and Precautions (5.5)].

Accidental Injection

Advise patients to seek immediate medical care in the case of accidental injection. Since epinephrine is a strong vasoconstrictor when injected into the digits, hands or feet, treatment should be directed at vasodilation if there is such an accidental injection to these areas [see Warnings and Precautions (5.2)].

Serious Infections at the Injection Site

Rare cases of skin and soft tissue infections, including necrotizing fasciitis and myonecrosis caused by Clostridia (gas gangrene), have been reported at the injection site following epinephrine injection for anaphylaxis. Advise patients to seek medical care if they develop signs or symptoms of infection, such as persistent redness, warmth, swelling, or tenderness, at the epinephrine injection site [see Warnings and Precautions (5.3)].

Pregnancy and Breastfeeding

Inform patients that epinephrine injection has not been studied in pregnant women or breastfeeding mothers so the effects of epinephrine injection on pregnant women or breastfed infants are not known. Instruct patients to tell their healthcare provider if they are pregnant, become pregnant, or are thinking about becoming pregnant. Instruct patients to tell their healthcare provider if they plan to breastfeed their infant [see Use in Specific Populations (8.1, 8.2)].

Storage and Handling

Instruct patients to inspect the epinephrine solution visually through the viewing window periodically. Replace epinephrine injection, USP auto-injector if the epinephrine solution appears discolored (pinkish or brown), cloudy, or contains particles. Epinephrine is light sensitive, store in the outer case provided to protect it from light. Instruct patients that epinephrine injection, USP auto-injector must be properly disposed of once the blue caps have been removed or after use [see How Supplied/Storage and Handling (16)].

Complete patient information, including dosage, directions for proper administration and precautions are provided inside each epinephrine injection carton.

Manufactured by:

Hospira, Inc.

McPherson, KS 67460

Distributed by:

Amneal Pharmaceuticals LLC

Bridgewater, NJ 08807

© 2021 Amneal Pharmaceuticals LLC. All rights reserved.

For inquiries call 1-877-835-5472

Patient Information

EPINEPHRINE injection (ep-in-eph-rine),

for intramuscular or subcutaneous use

For allergic emergencies (anaphylaxis)

Read this Patient Information leaflet carefully before you use epinephrine injection, and each time you get a refill. There may be new information. You, your parent, caregiver, or others who may be in a position to administer epinephrine injection should know how to use it before you have an allergic emergency.

This information does not take the place of talking with your healthcare provider about your medical condition or your treatment.

What is the most important information I should know about epinephrine injection?

1. Epinephrine injection contains epinephrine, a medicine used to treat allergic emergencies (anaphylaxis). Anaphylaxis can be life-threatening, can happen within minutes, and can be caused by stinging and biting insects, allergy injections, foods, medicines, exercise, or other unknown causes. Symptoms of an anaphylaxis may include:

- trouble breathing
- wheezing
- hoarseness (changes in the way your voice sounds)
- hives (raised reddened rash that may itch)
- severe itching
- swelling of your face, lips, mouth, or tongue
- skin rash, redness, or swelling
- fast heartbeat
- weak pulse
- feeling very anxious
- confusion
- stomach pain
- losing control of urine or bowel movements (incontinence)
- diarrhea or stomach cramps
- dizziness, fainting, or “passing out” (unconsciousness)

2. Always carry your epinephrine injection with you because you may not know when anaphylaxis may happen. Talk to your healthcare provider if you need additional units to keep at work, school, or other locations. Tell your family members, caregivers, and others where you keep your epinephrine injection and how to use it before you need it. You may be unable to speak in an allergic emergency.

3. When you have an allergic emergency (anaphylaxis)

- Use epinephrine injection right away.
- Get emergency medical help right away. You may need further medical attention. You may need to use a second epinephrine injection if symptoms continue or recur. Only a healthcare provider should give additional doses of epinephrine if you need more than 2 injections for a single anaphylaxis episode.

What is epinephrine injection?

- Epinephrine injection is a disposable, prefilled automatic injection device (auto-injector) used to treat life-threatening, allergic emergencies including anaphylaxis in people who are at risk for or have a history of serious allergic emergencies. Each device contains a single dose of epinephrine.
- Epinephrine injection is for immediate self (or caregiver) administration and does not take the place of emergency medical care. You should get emergency medical help right away after using epinephrine injection.
- Epinephrine injection is for people who have been prescribed this medicine by their healthcare provider.
- The epinephrine injection 0.3 mg auto-injector is for patients who weigh 66 pounds or more (30 kilograms or more).
- The epinephrine injection 0.15 mg auto-injector is for patients who weigh about 33 to 66 pounds (15 to 30 kilograms).
- It is not known if epinephrine injection is safe and effective in children who weigh less than 33 pounds (15 kilograms).

Before using epinephrine injection, tell your healthcare provider about all your medical conditions, especially if you:

- have heart problems or high blood pressure
- have diabetes
- have thyroid problems
- have asthma
- have a history of depression
- have Parkinson's disease
- have any other medical conditions
- are pregnant or plan to become pregnant. It is not known if epinephrine will harm your unborn baby.
- are breastfeeding or plan to breastfeed. It is not known if epinephrine passes into your breast milk.

Tell your healthcare provider about all the medicines you take, including prescription and over-the-counter medicines, vitamins and herbal supplements. Tell your healthcare provider of all known allergies.

Especially tell your healthcare provider if you take certain asthma medicines.

Epinephrine injection and other medicines may affect each other, causing side effects. Epinephrine injection may affect the way other medicines work, and other medicines may affect how epinephrine injection works.

Know the medicines you take. Keep a list of them to show your healthcare provider and pharmacist when you get a new medicine.

Use your epinephrine injection for treatment of anaphylaxis as prescribed by your healthcare provider, regardless of your medical conditions or the medicine you take.

How should I use epinephrine injection?

- Each epinephrine injection contains only 1 dose of medicine.
- Epinephrine injection should only be injected into the middle of the outer thigh (upper leg). It can be injected through clothing, if needed.
- Read the Instructions for Use at the end of this Patient Information Leaflet for information about the right way to use epinephrine injection.
- Your healthcare provider will show you how to safely use epinephrine injection.
- Use epinephrine injection exactly as your healthcare provider tells you to use it. You may need to use a second epinephrine injection if symptoms continue or recur. Only a healthcare provider should give additional doses of epinephrine if you need more than 2 injections for a single anaphylaxis episode.
- Caution: Never put your thumb, fingers, or hand over the red tip. Never press or push the red tip with your thumb, fingers, or hand. The needle comes out of the red tip. Accidental injection into finger, hands, or feet may cause a loss of blood flow to those areas. If this happens, go immediately to the nearest emergency room. Tell the healthcare provider where on your body you received the accidental injection.
- Your epinephrine injection comes packaged in a carton containing 1 or 2 epinephrine injection.
- You may request a separate Trainer, that comes packaged with instructions. Additional video instructions on the use of epinephrine injection are available from www.epinephrineautoinject.com. The epinephrine injection, USP auto-injector Trainer has a beige color. The beige epinephrine injection Trainer contains no medicine and no needle. Practice with your epinephrine injection Trainer before an allergic emergency happens to make sure you are able to safely use the real epinephrine injection in an emergency. Always carry your real epinephrine injection with you in case of an allergic emergency.
- Do not drop the carrying case or epinephrine injection. If the carrying case or epinephrine injection is dropped, check for damage and leakage. Throw away (dispose of) epinephrine injection and the carrying case, and replace if damage or leakage is noticed or suspected.

What are the possible side effects of epinephrine injection?

Epinephrine injection may cause serious side effects.

- Epinephrine injection should only be injected into the middle of your outer thigh (upper leg). Do not inject epinephrine injection into your:
  - veins
  - buttocks
  - fingers, toes, hands or feet.

If you accidentally inject epinephrine injection into any other part of your body, go to the nearest emergency room right away. Tell the healthcare provider where on your body you received the accidental injection.

- Rarely, people who use epinephrine injection may develop infections at the injection site within a few days of an injection. Some of these infections can be serious. Call your healthcare provider right away if you have any of the following at an injection site:
  - redness that does not go away
  - swelling
  - tenderness
  - the area feels warm to the touch

- Cuts on the skin, bent needles, and needles that remain in the skin after the injection, have happened in young children who do not cooperate and kick or move during an injection. If you inject a young child with epinephrine injection, hold their leg firmly in place before and during the injection to prevent injuries. Ask your healthcare provider to show you how to properly hold the leg of a young child during an injection.

- If you have certain medical conditions, or take certain medicines, your condition may get worse or you may have more or longer lasting side effects when you use epinephrine injection. Talk to your healthcare provider about all your medical conditions.

Common side effects of epinephrine injection include:

- faster, irregular or “pounding” heartbeat
- sweating
- headache
- weakness
- shakiness
- paleness
- feelings of over excitement, nervousness, or anxiety
- dizziness
- nausea or vomiting
- breathing problems

These side effects may go away with rest. Tell your healthcare provider if you have any side effect that bothers you or that does not go away.

These are not all the possible side effects of epinephrine injection. For more information, ask your healthcare provider or pharmacist.

Call your doctor for medical advice about side effects. You may report side effects to FDA at 1-800-FDA-1088.

How should I store epinephrine injection?

- Store epinephrine injection at room temperature between 68°F to 77° F (20°C to 25° C).
- Protect from light.
- Do not expose to extreme heat or cold. For example, do not store in your vehicle’s glove box and do not store in the refrigerator or freezer.
- Examine the contents in the clear viewing window of your epinephrine injection periodically. The solution should be clear. If the solution is discolored (pinkish or brown), cloudy or contains solid particles, replace the unit.
- Always keep your epinephrine injection in the carrying case to protect it from damage. The carrying case is not waterproof.
- The two blue end caps help to prevent accidental injection. Do not remove the blue end caps until you are ready to use epinephrine injection.
- Your epinephrine injection has an expiration date. Replace it before the expiration date.
- Throw away (dispose of) expired, unwanted, or unused epinephrine injections in an FDA-cleared sharps disposal container. Do not throw away epinephrine injection in your household trash. If you do not have an FDA-cleared sharps disposal container, you may use a household container that is:
  - Made of heavy-duty plastic,
  - Can be closed with a tight-fitting, puncture-resistant lid, without sharps being able to come out,
  - Upright and stable during use,
  - Leak-resistant, and
  - Properly labeled to warn of hazardous waste inside the container.
  When your sharps disposal container is almost full, you will need to follow your community guidelines for the right way to dispose of your sharps disposal container. There may be state or local laws about how you should throw away used needles and syringes. For more information about safe sharps disposal, and for specific information about sharps disposal in the state that you live in, go to the FDA’s website at: http://www.fda.gov/safesharpsdisposal Visit the FDA’s website (https://www.fda.gov/drugs/safe-disposal-medicines/disposal- unused-medicines-what-you-should-know) for more information about how to throw away (dispose of) unused, unwanted or expired medicines.

Keep epinephrine injection and all medicines out of the reach of children.

General information about the safe and effective use of epinephrine injection:

Medicines are sometimes prescribed for purposes other than those listed in a Patient Information leaflet. Do not use epinephrine injection for a condition for which it was not prescribed. Do not give epinephrine injection to other people.

This Patient Information Leaflet summarizes the most important information about epinephrine injection. If you would like more information, talk to your healthcare provider. You can ask your pharmacist or healthcare provider for information about epinephrine injection that is written for health professionals.

What are the ingredients in epinephrine injection?

Active Ingredient: epinephrine

Inactive Ingredients: sodium chloride, chlorobutanol, sodium bisulfite, hydrochloric acid and sodium hydroxide, and water.

For more information and video instructions on the use of epinephrine injection go to www.epinephrineautoinject.com or call 1-877-835-5472.

Important Information

- The epinephrine injection 0.3 mg has a yellow colored label.
- The epinephrine injection 0.15 mg has an orange colored label.
- The epinephrine injection Trainer has a beige color, and contains no medicine and no needle.
- Your epinephrine injection is designed to work through clothing.
- The two blue end caps on epinephrine injection help to prevent accidental injection of the device. Do not remove the blue end caps until you are ready to use it.
- Only inject into the middle of the outer thigh (upper leg). Never inject into any other part of the body.
- Never put your thumb, fingers, or your hand over the red tip. The needle comes out of the red tip.
- If an accidental injection happens, get medical help right away.
- Do not place patient information or any other foreign objects in carrier with the epinephrine injection, as this may prevent you from removing the auto-injector for use.

This Patient Information has been approved by the U.S. Food and Drug Administration
Rev. 02-2021-03

Instructions for Use

EPINEPHRINE injection (ep-in-eph-rine)

for intramuscular or subcutaneous use

For allergic emergencies (anaphylaxis)

Read this Instructions for Use carefully before you use epinephrine injection and each time you get a refill. There may be new information. Before you need to use your epinephrine injection, make sure your healthcare provider shows you the right way to use it. Parents, caregivers, and others who may be in a position to administer epinephrine injection should also understand how to use it well. This information does not take the place of talking to your healthcare provider about your medical condition or your treatment. If you have any questions, ask your healthcare provider.

Your epinephrine injection

Step 1. Prepare epinephrine injection for injection

- Remove epinephrine injection from its protective carrying case.
- Pull off blue end caps. You will now see a red tip. Grasp the epinephrine injection in your fist with the red tip pointing downward. See Figure A.

Note:

- The needle comes out of the red tip.
- To avoid an accidental injection, never put your thumb, fingers, or hand over the red tip. If an accidental injection happens, get medical help right away.

Step 2. Administer epinephrine injection

- If you are administering epinephrine injection to a young child, hold the leg firmly in place and limit movement prior to and while administering an injection.
- Put the red tip against the middle of the outer thigh (upper leg) at a 90° angle (perpendicular) to the thigh.
- Press down hard and hold firmly against the thigh for approximately 10 seconds to deliver the medicine. See Figure B.

- Only inject into the middle of the outer thigh. Do not inject into any other part of the body.
- Remove epinephrine injection from the thigh.
- Massage the area for 10 seconds.
- Check the red tip. The injection is complete and you have received the correct dose of the medicine if you see the needle sticking out of the red tip. If you do not see the needle repeat Step 2.

Step 3. Get emergency medical help right away. You may need further medical attention. You may need to use a second epinephrine injection if symptoms continue or recur.

Step 4. After use Disposal

Carefully cover the needle with the carrying case.

- Lay the labeled half of the carrying case cover down on a flat surface. Use one hand to carefully slide the end of the epinephrine injection needle first, into the labeled carrying case cover. See Figure C.

- After the needle is inside the labeled cover, push the unlabeled half of the carrying case cover firmly over the non-needle end of the epinephrine injection . See Figure D.

- Take your used epinephrine injection with you when you go to see a healthcare provider.
- Tell the healthcare provider that you have received an injection of epinephrine. Show the healthcare provider where you received the injection.
- Give your used epinephrine injection to the healthcare provider for inspection and proper disposal.
- Ask for a refill, if needed.

Note:

- Epinephrine injection is a single-use injectable device that delivers a fixed dose of epinephrine. Epinephrine injection cannot be reused. Do not attempt to reuse epinephrine injection after the device has been activated. It is normal for most of the medicine to remain in the auto-injector after the dose is injected. The correct dose has been administered if you see the needle sticking out of the red tip.
- A separate epinephrine injection Trainer is available. The epinephrine injection Trainer has a beige color. The beige epinephrine injection Trainer contains no medicine and no needle. Practice with your epinephrine injection Trainer, but always carry your real epinephrine injection in case of an allergic emergency.
- If you will be administering epinephrine injection to a young child, ask your healthcare provider to show you how to properly hold the leg in place while administering a dose.
- Do not try to take epinephrine injection.

For more information and video instructions on the use of epinephrine injection, go to www.epinephrineautoinject.com or call 1-877-835-5472.

This Patient Information and Instructions for Use has been approved by the U.S. Food and Drug Administration.

© 2021 Amneal Pharmaceuticals LLC. All rights reserved.

Manufactured by:
Hospira, Inc.
McPherson, KS 67460

Distributed by:
Amneal Pharmaceuticals LLC
Bridgewater, NJ 08807

Revised 02-2021-03

Albuterol Sulfate Inhalation Aerosol HFA with Dose Indicator

FOR ORAL INHALATION ONLY

Prescribing Information

DESCRIPTION

The active component of Albuterol Sulfate Inhalation Aerosol is albuterol sulfate, USP racemic α ^1 [(tert-Butylamino)methyl]-4-hydroxy- m-xylene-α,α'-diol sulfate (2:1)(salt), a relatively selective beta 2-adrenergic bronchodilator having the following chemical structure:

Albuterol sulfate is the official generic name in the United States. The World Health Organization recommended name for the drug is salbutamol sulfate. The molecular weight of albuterol sulfate is 576.7, and the empirical formula is (C13H21NO3)2•H2SO4. Albuterol sulfate is a white to off-white crystalline solid. It is soluble in water and slightly soluble in ethanol. Albuterol Sulfate Inhalation Aerosol is a pressurized metered-dose aerosol unit for oral inhalation. It contains a microcrystalline suspension of albuterol sulfate in propellant HFA-134a (1,1,1,2-tetrafluoroethane), ethanol, and oleic acid.

Each actuation delivers 120 mcg albuterol sulfate, USP from the valve and 108 mcg albuterol sulfate, USP from the mouthpiece (equivalent to 90 mcg of albuterol base from the mouthpiece). Each canister provides 200 inhalations. It is recommended to prime the inhaler before using for the first time and in cases where the inhaler has not been used for more than 2 weeks by releasing four “test sprays” into the air, away from the face.

This product does not contain chlorofluorocarbons (CFCs) as the propellant.

CLINICAL PHARMACOLOGY

Mechanism of Action In vitro studies and in vivo pharmacologic studies have demonstrated that albuterol has a preferential effect on beta2-adrenergic receptors compared with isoproterenol. While it is recognized that beta2-adrenergic receptors are the predominant receptors on bronchial smooth muscle, data indicate that there is a population of beta2-receptors in the human heart existing in a concentration between 10% and 50% of cardiac beta-adrenergic receptors. The precise function of these receptors has not been established. (See WARNINGS, Cardiovascular Effects section.)

Activation of beta2-adrenergic receptors on airway smooth muscle leads to the activation of adenylcyclase and to an increase in the intracellular concentration of cyclic-3',5'-adenosine monophosphate (cyclic AMP). This increase of cyclic AMP leads to the activation of protein kinase A, which inhibits the phosphorylation of myosin and lowers intracellular ionic calcium concentrations, resulting in relaxation. Albuterol relaxes the smooth muscles of all airways, from the trachea to the terminal bronchioles. Albuterol acts as a functional antagonist to relax the airway irrespective of the spasmogen involved, thus protecting against all bronchoconstrictor challenges. Increased cyclic AMP concentrations are also associated with the inhibition of release of mediators from mast cells in the airway.

Albuterol has been shown in most clinical trials to have more effect on the respiratory tract, in the form of bronchial smooth muscle relaxation, than isoproterenol at comparable doses while producing fewer cardiovascular effects. Controlled clinical studies and other clinical experience have shown that inhaled albuterol, like other beta-adrenergic agonist drugs, can produce a significant cardiovascular effect in some patients, as measured by pulse rate, blood pressure, symptoms, and/or electrocardiographic changes.

Preclinical Intravenous studies in rats with albuterol sulfate have demonstrated that albuterol crosses the blood-brain barrier and reaches brain concentrations amounting to approximately 5% of the plasma concentrations. In structures outside the blood-brain barrier (pineal and pituitary glands), albuterol concentrations were found to be 100 times those in the whole brain.

Studies in laboratory animals (minipigs, rodents, and dogs) have demonstrated the occurrence of cardiac arrhythmias and sudden death (with histologic evidence of myocardial necrosis) when beta2-agonist and methylxanthines were administered concurrently. The clinical significance of these findings is unknown.

Propellant HFA-134a is devoid of pharmacological activity except at very high doses in animals (380-1300 times the maximum human exposure based on comparisons of AUC values), primarily producing ataxia, tremors, dyspnea, or salivation. These are similar to effects produced by the structurally related chlorofluorocarbons (CFCs), which have been used extensively in metered dose inhalers.

In animals and humans, propellant HFA-134a was found to be rapidly absorbed and rapidly eliminated, with an elimination half-life of 3 to 27 minutes in animals and 5 to 7 minutes in humans. Time to maximum plasma concentration (Tmax) and mean residence time are both extremely short, leading to a transient appearance of HFA-134a in the blood with no evidence of accumulation.

PHARMACOKINETICS

Pharmacokinetics In a single-dose bioavailability study which enrolled six healthy, male volunteers, transient low albuterol levels (close to the lower limit of quantitation) were observed after administration of two puffs from both Albuterol Sulfate Inhalation Aerosol and a CFC 11/12 propelled albuterol inhaler. No formal pharmacokinetic analyses were possible for either treatment, but systemic albuterol levels appeared similar.

Clinical Trials In a 12-week, randomized, double-blind, double-dummy, active- and placebo-controlled trial, 565 patients with asthma were evaluated for the bronchodilator efficacy of Albuterol Sulfate Inhalation Aerosol (193 patients) in comparison to a CFC 11/12 propelled albuterol inhaler (186 patients) and an HFA-134a placebo inhaler (186 patients).

Serial FEV 1 measurements (shown below as percent change from test-day baseline) demonstrated that two inhalations of Albuterol Sulfate Inhalation Aerosol produced significantly greater improvement in pulmonary function than placebo and produced outcomes which were clinically comparable to a CFC 11/12 propelled albuterol inhaler.

The mean time to onset of a 15% increase in FEV 1 was 6 minutes and the mean time to peak effect was 50 to 55 minutes. The mean duration of effect as measured by a 15% increase in FEV 1 was 3 hours. In some patients, duration of effect was as long as 6 hours.

In another clinical study in adults, two inhalations of Albuterol Sulfate Inhalation Aerosol taken 30 minutes before exercise prevented exercise-induced bronchospasm as demonstrated by the maintenance of FEV 1 within 80% of baseline values in the majority of patients.

In a 4-week, randomized, open-label trial, 63 children, 4 to 11 years of age, with asthma were evaluated for the bronchodilator efficacy of Albuterol Sulfate Inhalation Aerosol (33 pediatric patients) in comparison to a CFC 11/12 propelled albuterol inhaler (30 pediatric patients).

Serial FEV 1 measurements as percent change from test-day baseline demonstrated that two inhalations of Albuterol Sulfate Inhalation Aerosol produced outcomes which were clinically comparable to a CFC 11/12 propelled albuterol inhaler.

The mean time to onset of a 12% increase in FEV 1 for Albuterol Sulfate Inhalation Aerosol was 7 minutes and the mean time to peak effect was approximately 50 minutes. The mean duration of effect as measured by a 12% increase in FEV 1 was 2.3 hours. In some pediatric patients, duration of effect was as long as 6 hours.

In another clinical study in pediatric patients, two inhalations of Albuterol Sulfate Inhalation Aerosol taken 30 minutes before exercise provided comparable protection against exercise-induced bronchospasm as a CFC 11/12 propelled albuterol inhaler.

INDICATIONS AND USAGE

Albuterol Sulfate Inhalation Aerosol is indicated in adults and children 4 years of age and older for the treatment or prevention of bronchospasm with reversible obstructive airway disease and for the prevention of exercise-induced bronchospasm.

CONTRAINDICATIONS

Albuterol Sulfate Inhalation Aerosol is contraindicated in patients with a history of hypersensitivity to albuterol or any other Albuterol Sulfate Inhalation Aerosol components.

WARNINGS

1. Paradoxical Bronchospasm: Inhaled albuterol sulfate can produce paradoxical bronchospasm that may be life threatening. If paradoxical bronchospasm occurs, Albuterol Sulfate Inhalation Aerosol should be discontinued immediately and alternative therapy instituted. It should be recognized that paradoxical bronchospasm, when associated with inhaled formulations, frequently occurs with the first use of a new canister.
2. Deterioration of Asthma: Asthma may deteriorate acutely over a period of hours or chronically over several days or longer. If the patient needs more doses of Albuterol Sulfate Inhalation Aerosol than usual, this may be a marker of destabilization of asthma and requires re-evaluation of the patient and treatment regimen, giving special consideration to the possible need for anti-inflammatory treatment, e.g., corticosteroids.
3. Use of Anti-inflammatory Agents: The use of beta-adrenergic-agonist bronchodilators alone may not be adequate to control asthma in many patients. Early consideration should be given to adding anti-inflammatory agents, e.g., corticosteroids, to the therapeutic regimen.
4. Cardiovascular Effects: Albuterol Sulfate Inhalation Aerosol, like other beta-adrenergic agonists, can produce clinically significant cardiovascular effects in some patients as measured by pulse rate, blood pressure, and/or symptoms. Although such effects are uncommon after administration of Albuterol Sulfate Inhalation Aerosol at recommended doses, if they occur, the drug may need to be discontinued. In addition, beta-agonists have been reported to produce ECG changes, such as flattening of the T wave, prolongation of the QTc interval, and ST segment depression. The clinical significance of these findings is unknown. Therefore, Albuterol Sulfate Inhalation Aerosol, like all sympathomimetic amines, should be used with caution in patients with cardiovascular disorders, especially coronary insufficiency, cardiac arrhythmias, and hypertension.
5. Do Not Exceed Recommended Dose: Fatalities have been reported in association with excessive use of inhaled sympathomimetic drugs in patients with asthma. The exact cause of death is unknown, but cardiac arrest following an unexpected development of a severe acute asthmatic crisis and subsequent hypoxia is suspected.
6. Immediate Hypersensitivity Reactions: Immediate hypersensitivity reactions may occur after administration of albuterol sulfate, as demonstrated by rare cases of urticaria, angioedema, rash, bronchospasm, anaphylaxis, and oropharyngeal edema.

PRECAUTIONS

GENERAL PRECAUTIONS

General Albuterol sulfate, as with all sympathomimetic amines, should be used with caution in patients with cardiovascular disorders, especially coronary insufficiency, cardiac arrhythmias, and hypertension; in patients with convulsive disorders, hyperthyroidism, or diabetes mellitus; and in patients who are unusually responsive to sympathomimetic amines. Clinically significant changes in systolic and diastolic blood pressure have been seen in individual patients and could be expected to occur in some patients after use of any beta-adrenergic bronchodilator.

Large doses of intravenous albuterol have been reported to aggravate preexisting diabetes mellitus and ketoacidosis. As with other beta-agonists, albuterol may produce significant hypokalemia in some patients, possibly through intracellular shunting, which has the potential to produce adverse cardiovascular effects. The decrease is usually transient, not requiring supplementation.

PATIENT COUNSELING INFORMATION

Information for Patients See illustrated Patient's Instructions for Use. SHAKE WELL BEFORE USING. Patients should be given the following information:

It is recommended to prime the inhaler before using for the first time and in cases where the inhaler has not been used for more than 2 weeks by releasing four “test sprays” into the air, away from the face.

KEEPING THE PLASTIC MOUTHPIECE CLEAN IS VERY IMPORTANT TO PREVENT MEDICATION BUILDUP AND BLOCKAGE. THE MOUTHPIECE SHOULD BE WASHED, SHAKEN TO REMOVE EXCESS WATER, AND AIR DRIED THOROUGHLY AT LEAST ONCE A WEEK. INHALER MAY CEASE TO DELIVER MEDICATION IF NOT PROPERLY CLEANED.

The mouthpiece should be cleaned (with the canister removed) by running warm water through the top and bottom for 30 seconds at least once a week. The mouthpiece must be shaken to remove excess water, then air dried thoroughly (such as overnight). Blockage from medication buildup or improper medication delivery may result from failure to thoroughly air dry the mouthpiece.

If the mouthpiece should become blocked (little or no medication coming out of the mouthpiece), the blockage may be removed by washing as described above.

If it is necessary to use the inhaler before it is completely dry, shake off excess water, replace canister, test spray twice away from face, and take the prescribed dose. After such use, the mouthpiece should be rewashed and allowed to air dry thoroughly.

The action of Albuterol Sulfate Inhalation Aerosol should last up to 4 to 6 hours. Albuterol Sulfate Inhalation Aerosol should not be used more frequently than recommended. Do not increase the dose or frequency of doses of Albuterol Sulfate Inhalation Aerosol without consulting your physician. If you find that treatment with Albuterol Sulfate Inhalation Aerosol becomes less effective for symptomatic relief, your symptoms become worse, and/or you need to use the product more frequently than usual, medical attention should be sought immediately. While you are taking Albuterol Sulfate Inhalation Aerosol, other inhaled drugs and asthma medications should be taken only as directed by your physician.

Common adverse effects of treatment with inhaled albuterol include palpitations, chest pain, rapid heart rate, tremor, or nervousness. If you are pregnant or nursing, contact your physician about use of Albuterol Sulfate Inhalation Aerosol. Effective and safe use of Albuterol Sulfate Inhalation Aerosol includes an understanding of the way that it should be administered. Use Albuterol Sulfate Inhalation Aerosol only with the actuator supplied with the product. Discard the canister after 200 sprays have been used.

In general, the technique for administering Albuterol Sulfate Inhalation Aerosol to children is similar to that for adults. Children should use Albuterol Sulfate Inhalation Aerosol under adult supervision, as instructed by the patient's physician. (See Patient's Instructions for Use.)

Drug Interactions

1. Beta-Blockers: Beta-adrenergic-receptor blocking agents not only block the pulmonary effect of beta-agonists, such as Albuterol Sulfate Inhalation Aerosol, but may produce severe bronchospasm in asthmatic patients. Therefore, patients with asthma should not normally be treated with beta-blockers. However, under certain circumstances, e.g., as prophylaxis after myocardial infarction, there may be no acceptable alternatives to the use of beta-adrenergic blocking agents in patients with asthma. In this setting, cardioselective beta-blockers should be considered, although they should be administered with caution.
2. Diuretics: The ECG changes and/or hypokalemia which may result from the administration of nonpotassium-sparing diuretics (such as loop or thiazide diuretics) can be acutely worsened by beta-agonists, especially when the recommended dose of the beta-agonist is exceeded. Although the clinical significance of these effects is not known, caution is advised in the coadministration of beta-agonists with nonpotassium-sparing diuretics.
3. Albuterol-Digoxin: Mean decreases of 16% and 22% in serum digoxin levels were demonstrated after single-dose intravenous and oral administration of albuterol, respectively, to normal volunteers who had received digoxin for 10 days. The clinical significance of these findings for patients with obstructive airway disease who are receiving albuterol and digoxin on a chronic basis is unclear; nevertheless, it would be prudent to carefully evaluate the serum digoxin levels in patients who are currently receiving digoxin and albuterol.
4. Monoamine Oxidase Inhibitors or Tricyclic Antidepressants: Albuterol Sulfate Inhalation Aerosol should be administered with extreme caution to patients being treated with monoamine oxidase inhibitors or tricyclic antidepressants, or within 2 weeks of discontinuation of such agents, because the action of albuterol on the cardiovascular system may be potentiated.

Carcinogenesis, Mutagenesis, and Impairment of Fertility

In a 2-year study in SPRAGUE-DAWLEY® rats, albuterol sulfate caused a dose-related increase in the incidence of benign leiomyomas of the mesovarium at the above dietary doses of 2 mg/kg (approximately 15 times the maximum recommended daily inhalation dose for adults on a mg/m^2 basis and approximately 6 times the maximum recommended daily inhalation dose for children on a mg/m^2 basis). In another study this effect was blocked by the coadministration of propranolol, a nonselective beta-adrenergic antagonist. In an 18-month study in CD-1 mice, albuterol sulfate showed no evidence of tumorigenicity at dietary doses of up to 500 mg/kg (approximately 1700 times the maximum recommended daily inhalation dose for adults on a mg/m^2 basis and approximately 800 times the maximum recommended daily inhalation dose for children on a mg/m^2 basis). In a 22-month study in Golden Hamsters, albuterol sulfate showed no evidence of tumorigenicity at dietary doses of up to 50 mg/kg (approximately 225 times the maximum recommended daily inhalation dose for adults on a mg/m^2 basis and approximately 110 times the maximum recommended daily inhalation dose for children on a mg/m^2 basis).

Albuterol sulfate was not mutagenic in the Ames test or a mutation test in yeast. Albuterol sulfate was not clastogenic in a human peripheral lymphocyte assay or in an AH1 strain mouse micronucleus assay.

Reproduction studies in rats demonstrated no evidence of impaired fertility at oral doses up to 50 mg/kg (approximately 340 times the maximum recommended daily inhalation dose for adults on a mg/m^2 basis).

Pregnancy Teratogenic Effects Pregnancy

Albuterol sulfate has been shown to be teratogenic in mice. A study in CD-1 mice given albuterol sulfate subcutaneously showed cleft palate formation in 5 of 111 (4.5%) fetuses at 0.25 mg/kg (less than the maximum recommended daily inhalation dose for adults on a mg/m^2 basis) and in 10 of 108 (9.3%) fetuses at 2.5 mg/kg (approximately 8 times the maximum recommended daily inhalation dose for adults on a mg/m^2 basis). The drug did not induce cleft palate formation at a dose of 0.025 mg/kg (less than the maximum recommended daily inhalation dose for adults on a mg/m^2 basis). Cleft palate also occurred in 22 of 72 (30.5%) fetuses from females treated subcutaneously with 2.5 mg/kg of isoproterenol (positive control).

A reproduction study in Stride Dutch rabbits revealed cranioschisis in 7 of 19 (37%) fetuses when albuterol sulfate was administered orally at 50 mg/kg dose (approximately 680 times the maximum recommended daily inhalation dose for adults on a mg/m^2 basis).

In an inhalation reproduction study in SPRAGUE-DAWLEY rats, the albuterol sulfate/HFA-134a formulation did not exhibit any teratogenic effects at 10.5 mg/kg (approximately 70 times the maximum recommended daily inhalation dose for adults on a mg/m^2 basis).

A study in which pregnant rats were dosed with radiolabeled albuterol sulfate demonstrated that drug-related material is transferred from the maternal circulation to the fetus.

There are no adequate and well-controlled studies of Albuterol Sulfate Inhalation Aerosol or albuterol sulfate in pregnant women. Albuterol Sulfate Inhalation Aerosol should be used during pregnancy only if the potential benefit justifies the potential risk to the fetus.

During worldwide marketing experience, various congenital anomalies, including cleft palate and limb defects, have been reported in the offspring of patients being treated with albuterol. Some of the mothers were taking multiple medications during their pregnancies. Because no consistent pattern of defects can be discerned, a relationship between albuterol use and congenital anomalies has not been established.

Use in Labor and Delivery

Because of the potential for beta-agonist interference with uterine contractility, use of Albuterol Sulfate Inhalation Aerosol for relief of bronchospasm during labor should be restricted to those patients in whom the benefits clearly outweigh the risk.

Tocolysis: Albuterol has not been approved for the management of preterm labor. The benefit:risk ratio when albuterol is administered for tocolysis has not been established. Serious adverse reactions, including pulmonary edema, have been reported during or following treatment of premature labor with beta2-agonists, including albuterol.

Nursing Mothers

Plasma levels of albuterol sulfate and HFA-134a after inhaled therapeutic doses are very low in humans, but it is not known whether the components of Albuterol Sulfate Inhalation Aerosol are excreted in human milk.

Because of the potential for tumorigenicity shown for albuterol in animal studies and lack of experience with the use of Albuterol Sulfate Inhalation Aerosol by nursing mothers, a decision should be made whether to discontinue nursing or to discontinue the drug, taking into account the importance of the drug to the mother. Caution should be exercised when albuterol sulfate is administered to a nursing woman.

Pediatrics

The safety and effectiveness of Albuterol Sulfate Inhalation Aerosol in pediatric patients below the age of 4 years have not been established.

Geriatrics

Albuterol Sulfate Inhalation Aerosol has not been studied in a geriatric population. As with other beta2-agonists, special caution should be observed when using Albuterol Sulfate Inhalation Aerosol in elderly patients who have concomitant cardiovascular disease that could be adversely affected by this class of drug.

ADVERSE REACTIONS

Adverse reaction information concerning Albuterol Sulfate Inhalation Aerosol is derived from a 12-week, double-blind, double-dummy study which compared Albuterol Sulfate Inhalation Aerosol, a CFC 11/12 propelled albuterol inhaler, and an HFA-134a placebo inhaler in 565 asthmatic patients. The following table lists the incidence of all adverse events (whether considered by the investigator drug related or unrelated to drug) from this study which occurred at a rate of 3% or greater in the Albuterol Sulfate Inhalation Aerosol treatment group and more frequently in the Albuterol Sulfate Inhalation Aerosol treatment group than in the placebo group. Overall, the incidence and nature of the adverse reactions reported for Albuterol Sulfate Inhalation Aerosol and a CFC 11/12 propelled albuterol inhaler were comparable.

Adverse Experience Incidences (% of patients) in a Large 12-week Clinical Trial*
Body System/ Adverse Event (Preferred Term) |  | Albuterol Sulfate Inhalation Aerosol (N=193) | CFC 11/12 Propelled Albuterol Inhaler (N=186) | HFA-134a Placebo Inhaler (N=186)
Application Site Disorders | Inhalation Site Sensation | 6 | 9 | 2
Application Site Disorders | Inhalation Taste Sensation | 4 | 3 | 3
Body as a Whole | Allergic Reaction/Symptoms | 6 | 4 | <1
Body as a Whole | Back Pain | 4 | 2 | 3
Body as a Whole | Fever | 6 | 2 | 5
Central and Peripheral Nervous System | Tremor | 7 | 8 | 2
Gastrointestinal System | Nausea | 10 | 9 | 5
Gastrointestinal System | Vomiting | 7 | 2 | 3
Heart Rate and Rhythm Disorder | Tachycardia | 7 | 2 | <1
Psychiatric Disorders | Nervousness | 7 | 9 | 3
Respiratory System Disorders | Respiratory Disorder (unspecified) | 6 | 4 | 5
Respiratory System Disorders | Rhinitis | 16 | 22 | 14
Respiratory System Disorders | Upper Resp Tract Infection | 21 | 20 | 18
Urinary System Disorder | Urinary Tract Infection | 3 | 4 | 2
*This table includes all adverse events (whether considered by the investigator drug related or unrelated to drug) which occurred at an incidence rate of at least 3% in the Albuterol Sulfate Inhalation Aerosol group and more frequently in the Albuterol Sulfate Inhalation Aerosol group than in the HFA-134a placebo inhaler group.

Adverse events reported by less than 3% of the patients receiving Albuterol Sulfate Inhalation Aerosol, and by a greater proportion of Albuterol Sulfate Inhalation Aerosol patients than placebo patients, which have the potential to be related to Albuterol Sulfate Inhalation Aerosol include: dysphonia, increased sweating, dry mouth, chest pain, edema, rigors, ataxia, leg cramps, hyperkinesia, eructation, flatulence, tinnitus, diabetes mellitus, anxiety, depression, somnolence, rash. Palpitation and dizziness have also been observed with Albuterol Sulfate Inhalation Aerosol.

Adverse events reported in a 4-week pediatric clinical trial comparing Albuterol Sulfate Inhalation Aerosol and a CFC 11/12 propelled albuterol inhaler occurred at a low incidence rate and were similar to those seen in the adult trials.

In small, cumulative dose studies, tremor, nervousness, and headache appeared to be dose related.

Rare cases of urticaria, angioedema, rash, bronchospasm, and oropharyngeal edema have been reported after the use of inhaled albuterol. In addition, albuterol, like other sympathomimetic agents, can cause adverse reactions such as hypertension, angina, vertigo, central nervous system stimulation, insomnia, headache, metabolic acidosis, and drying or irritation of the oropharynx.

To report SUSPECTED ADVERSE REACTIONS, contact Sandoz Inc., at 1-800-525-8747 or FDA at 1-800-FDA-1088 or www.fda.gov/medwatch.

OVERDOSAGE

The expected symptoms with overdosage are those of excessive beta-adrenergic stimulation and/or occurrence or exaggeration of any of the symptoms listed under ADVERSE REACTIONS, e.g., seizures, angina, hypertension or hypotension, tachycardia with rates up to 200 beats per minute, arrhythmias, nervousness, headache, tremor, dry mouth, palpitation, nausea, dizziness, fatigue, malaise, and insomnia.

Hypokalemia may also occur. As with all sympathomimetic medications, cardiac arrest and even death may be associated with abuse of Albuterol Sulfate Inhalation Aerosol. Treatment consists of discontinuation of Albuterol Sulfate Inhalation Aerosol together with appropriate symptomatic therapy. The judicious use of a cardioselective beta-receptor blocker may be considered, bearing in mind that such medication can produce bronchospasm. There is insufficient evidence to determine if dialysis is beneficial for overdosage of Albuterol Sulfate Inhalation Aerosol.

The oral median lethal dose of albuterol sulfate in mice is greater than 2000 mg/kg (approximately 6800 times the maximum recommended daily inhalation dose for adults on a mg/m^2 basis and approximately 3200 times the maximum recommended daily inhalation dose for children on a mg/m^2 basis). In mature rats, the subcutaneous median lethal dose of albuterol sulfate is approximately 450 mg/kg (approximately 3000 times the maximum recommended daily inhalation dose for adults on a mg/m^2 basis and approximately 1400 times the maximum recommended daily inhalation dose for children on a mg/m^2 basis). In young rats, the subcutaneous median lethal dose is approximately 2000 mg/kg (approximately 14,000 times the maximum recommended daily inhalation dose for adults on a mg/m^2 basis and approximately 6400 times the maximum recommended daily inhalation dose for children on a mg/m^2 basis). The inhalation median lethal dose has not been determined in animals.

DOSAGE AND ADMINISTRATION

For treatment of acute episodes of bronchospasm or prevention of asthmatic symptoms, the usual dosage for adults and children 4 years of age and older is two inhalations repeated every 4 to 6 hours. More frequent administration or a larger number of inhalations is not recommended. In some patients, one inhalation every 4 hours may be sufficient. Each actuation of Albuterol Sulfate Inhalation Aerosol delivers 108 mcg of albuterol sulfate (equivalent to 90 mcg of albuterol base) from the mouthpiece. It is recommended to prime the inhaler before using for the first time and in cases where the inhaler has not been used for more than 2 weeks by releasing four “test sprays” into the air, away from the face.

Exercise Induced Bronchospasm Prevention: The usual dosage for adults and children 4 years of age and older is two inhalations 15 to 30 minutes before exercise.

To maintain proper use of this product, it is important that the mouthpiece be washed and dried thoroughly at least once a week. The inhaler may cease to deliver medication if not properly cleaned and dried thoroughly (see PRECAUTIONS, Information for Patients section). Keeping the plastic mouthpiece clean is very important to prevent medication buildup and blockage. The inhaler may cease to deliver medication if not properly cleaned and air dried thoroughly. If the mouthpiece becomes blocked, washing the mouthpiece will remove the blockage.

If a previously effective dose regimen fails to provide the usual response, this may be a marker of destabilization of asthma and requires reevaluation of the patient and the treatment regimen, giving special consideration to the possible need for anti-inflammatory treatment, e.g., corticosteroids.

HOW SUPPLIED

Albuterol Sulfate Inhalation Aerosol is supplied as a pressurized aluminum canister, with an attached dose indicator, a yellow plastic actuator and orange dust cap each in boxes of one. Each actuation delivers 120 mcg of albuterol sulfate from the valve and 108 mcg of albuterol sulfate from the mouthpiece (equivalent to 90 mcg of albuterol base). Canisters with a labeled net weight of 6.7 g contain 200 inhalations (NDC 0781-7296-85).

Rx only. Store between 15° to 25°C (59° to 77°F). Store the inhaler with the mouthpiece down. For best results, canister should be at room temperature before use.

SHAKE WELL BEFORE USING.

The yellow actuator supplied with Albuterol Sulfate Inhalation Aerosol should not be used with any other product canisters, and actuator from other products should not be used with a Albuterol Sulfate Inhalation Aerosol canister. The correct amount of medication in each canister cannot be assured after 200 actuations and when the dose indicator display window shows zero, even though the canister is not completely empty. The canister should be discarded when the labeled number of actuations have been used.

WARNING: Avoid spraying in eyes. Contents under pressure. Do not puncture or incinerate. Exposure to temperatures above 120°F may cause bursting. Keep out of reach of children.

Albuterol Sulfate Inhalation Aerosol does not contain chlorofluorocarbons (CFCs) as the propellant.

Distributed by:
Sandoz Inc.
Princeton, NJ 08540

Copyright © 1996, 2011, 2012, 2017, 2018, 2020
All rights reserved. The trademarks depicted in this piece are owned by their respective companies.

Revised: 12/2020

INSTRUCTIONS FOR USE
Albuterol Sulfate (al-BYOO-ter-ole)
Inhalation Aerosol with Dose Indicator

Read this Instructions for Use before you start using Albuterol Sulfate Inhalation Aerosol and each time you get a refill. There may be new information. This information does not take the place of talking to your doctor about your medical condition or treatment. Your doctor should show you how your child should use Albuterol Sulfate Inhalation Aerosol.

Important Information:

- Albuterol Sulfate Inhalation Aerosol is for oral inhalation use only.
- Take Albuterol Sulfate Inhalation Aerosol exactly as your doctor tells you to.

Albuterol Sulfate Inhalation Aerosol comes as a canister with a dose indicator. The dose indicator is located on the top of the canister that fits into an actuator (See Figure A). The dose indicator display window will show you how many puffs of medicine you have left. A puff of medicine is released each time you press the center of the dose indicator.

- Do not use the Albuterol Sulfate Inhalation Aerosol actuator with a canister of medicine from any other inhaler.
- Do not use the Albuterol Sulfate Inhalation Aerosol canister with an actuator from any other inhaler.

Figure A

Before you use Albuterol Sulfate Inhalation Aerosol for the first time make sure that the pointer on the dose indicator is pointing to the right of the “200” inhalation mark in the dose indicator display window (See Figure A) .

Each canister of Albuterol Sulfate Inhalation Aerosol contains 200 puffs of medicine. This does not include the sprays of medicine used for priming your inhaler.

- The dose indicator display window will continue to move after every 10 puffs.
- The number in the dose indicator display window will continue to change after every 20 puffs.
- The color in the dose indicator display window will change to red, as shown in the shaded area, when there are only 20 puffs of medicine left in your inhaler (See Figure B) . This is when you need to refill your prescription or ask your doctor if you need another prescription for Albuterol Sulfate Inhalation Aerosol.

Figure B

Before using your Albuterol Sulfate Inhalation Aerosol for the first time, you should prime your inhaler. If you do not use your Albuterol Sulfate Inhalation Aerosol for more than 2 weeks, you should re-prime it before use.

- Remove the cap from the mouthpiece (See Figure C). Check inside the mouthpiece for objects before use.
- Make sure the canister is fully inserted into the actuator.
- Hold the inhaler in an upright position away from your face and shake the inhaler well.
- Press down fully on the center of the dose indicator to release a spray of medicine. You may hear a soft click from the dose indicator as it counts down during use.
- Repeat the priming step 3 more times to release a total of 4 sprays of medicine. Shake the inhaler well before each priming spray.
- After the 4 priming sprays, the dose indicator should be pointing to 200. There are now 200 puffs of medicine left in the canister.
- Your inhaler is now ready to use.

Using your Albuterol Sulfate Inhalation Aerosol inhaler:

Step 1: Shake the inhaler well before each use. Remove the cap from the mouthpiece (See Figure C). Check inside the mouthpiece for objects before use. Make sure the canister is fully inserted into the actuator.

Figure C

Step 2: Breathe out as fully as you comfortably can through your mouth. Hold the inhaler in the upright position with the mouthpiece pointing towards you and place the mouthpiece fully into the mouth (See Figure D). Close your lips around the mouthpiece.

Figure D

Step 3: While breathing in deeply and slowly, press down on the center of the dose indicator with your index finger until the canister stops moving in the actuator and a puff of medicine has been released (See Figure D). Then stop pressing the dose indicator.

Step 4: Hold your breath as long as you comfortably can, up to 10 seconds. Remove the inhaler from your mouth, and then breathe out.

Step 5: If your doctor has prescribed additional puffs of Albuterol Sulfate Inhalation Aerosol, wait 1 minute then shake the inhaler well. Repeat steps 3 through 5 in the section “ Using your Albuterol Sulfate Inhalation Aerosol inhaler”.

Step 6: Replace the cap right away after use.

Cleaning your Albuterol Sulfate Inhalation Aerosol inhaler:

It is very important that you keep the mouthpiece clean so that medicine will not build up and block the spray through the mouthpiece. Clean the mouthpiece 1 time each week or if your mouthpiece becomes blocked (See Figure F).

Step 1: Remove the canister from the actuator and take the cap off the mouthpiece. Do not clean the metal canister or let it get wet.

Step 2: Wash the mouthpiece through the top and bottom with warm running water for 30 seconds (See Figure E).

Figure E

Step 3: Shake off as much water from the mouthpiece as you can.

Step 4: Look in the mouthpiece to make sure any medicine buildup has been completely washed away. If the mouthpiece is blocked with buildup, little to no medicine will come out of the mouthpiece (See Figure F). If there is any buildup, repeat Steps 2 through 4 in the section “ Cleaning your Albuterol Sulfate Inhalation Aerosol inhaler”.

Figure F

Step 5: Let the mouthpiece air-dry such as overnight (Figure G). Do not put the canister back into the actuator if it is still wet.

Figure G

Step 6: When the mouthpiece is dry, put the canister back in the actuator and put the cap on the mouthpiece.

Note: If you need to use your Albuterol Sulfate Inhalation Aerosol inhaler before it is completely dry, put the canister back in the actuator and shake the inhaler well. Press down on the center of the dose indicator 2 times to release a total of 2 sprays into the air, away from your face. Take your dose as prescribed then clean and air-dry your inhaler as described in the section “ Cleaning your Albuterol Sulfate Inhalation Aerosol inhaler”.

How should I store Albuterol Sulfate Inhalation Aerosol?

- Store Albuterol Sulfate Inhalation Aerosol at room temperature between 59°F and 77°F (15°C and 25°C).
- Store with the mouthpiece down.
- Avoid exposing Albuterol Sulfate Inhalation Aerosol to extreme heat and cold.
- Do not puncture or burn the canister.
- Keep your Albuterol Sulfate Inhalation Aerosol inhaler and all medicines out of the reach of children.

Developed and Manufactured by:
Kindeva Drug Delivery L.P.
Northridge, CA 91324, USA

Distributed by:
Sandoz Inc.
Princeton, NJ 08540

Copyright © 1996, 2011, 2012, 2017, 2018, 2020All rights reserved.

This Instructions for Use has been approved by the U.S. Food and Drug Administration.

Revised: 12/2020

NITROGLYCERIN TABLETS

These highlights do not include all the information needed to use NITROGLYCERIN SUBLINGUAL TABLETS safely and effectively. See full prescribing information for NITROGLYCERIN SUBLINGUAL TABLETS

NITROGLYCERIN sublingual tablets, for oral use
Initial U.S. Approval: 1981

FULL PRESCRIBING INFORMATION

1 INDICATIONS AND USAGE

Nitroglycerin sublingual tablets are indicated for the acute relief of an attack or acute prophylaxis of angina pectoris due to coronary artery disease.

2 DOSAGE AND ADMINISTRATION

Administer one tablet under the tongue or in the buccal pouch at the first sign of an acute anginal attack. Allow tablet to dissolve without swallowing. One additional tablet may be administered every 5 minutes until relief is obtained. No more than three tablets are recommended within a 15-minute period. If the pain persists after a total of 3 tablets in a 15-minute period, or if the pain is different than is typically experienced, seek prompt medical attention.

Nitroglycerin sublingual tablets may be used prophylactically 5 to 10 minutes prior to engaging in activities that might precipitate an acute attack.

For patients with xerostomia, a small sip of water prior to placing the tablet under the tongue may help maintain mucosal hydration and aid dissolution of the tablet.

Administer nitroglycerin sublingual tablets at rest, preferably in the sitting position.

3 DOSAGE FORMS AND STRENGTHS

Nitroglycerin Sublingual Tablets, USP are supplied as white to off-white, round, flat-faced tablets in three strengths:

0.3 mg (Debossed with “1” on one side and “C” on the other)
0.4 mg (Debossed with “2” on one side and “C” on the other)
0.6 mg (Debossed with “3” on one side and “C” on the other)

4 CONTRAINDICATIONS

4.1 PDE-5-Inhibitors and sGC-Stimulators

Do not use nitroglycerin sublingual tablets in patients who are taking PDE-5 Inhibitors, such as avanafil, sildenafil, tadalafil, vardenafil hydrochloride. Concomitant use can cause severe hypotension, syncope, or myocardial ischemia [see Drug Interactions (7.1)].

Do not use nitroglycerin sublingual tablets in patients who are taking the soluble guanylate cyclase stimulators, such as riociguat. Concomitant use can cause hypotension.

4.2 Severe Anemia

Nitroglycerin sublingual tablets are contraindicated in patients with severe anemia (large doses of nitroglycerin may cause oxidation of hemoglobin to methemoglobin and could exacerbate anemia).

4.3 Increased Intracranial Pressure

Nitroglycerin sublingual tablets may precipitate or aggravate increased intracranial pressure and thus should not be used in patients with possible increased intracranial pressure (e.g., cerebral hemorrhage or traumatic brain injury).

4.4 Hypersensitivity

Nitroglycerin sublingual tablets are contraindicated in patients who are allergic to nitroglycerin, other nitrates or nitrites or any excipient.

4.5 Circulatory Failure and Shock

Nitroglycerin sublingual tablets are contraindicated in patients with acute circulatory failure or shock.

5 WARNINGS AND PRECAUTIONS

- Tolerance: Excessive use may lead to tolerance. (5.1)
- Hypotension: Severe hypotension may occur. (5.2)

5.1 Tolerance

Excessive use may lead to the development of tolerance. Only the smallest dose required for effective relief of the acute angina attack should be used. A decrease in therapeutic effect of sublingual nitroglycerin may result from use of long-acting nitrates.

5.2 Hypotension

Severe hypotension, particularly with upright posture, may occur with small doses of nitroglycerin particularly in patients with constrictive pericarditis, aortic or mitral stenosis, patients who may be volume-depleted, or are already hypotensive. Hypotension induced by nitroglycerin may be accompanied by paradoxical bradycardia and increased angina pectoris. Symptoms of severe hypotension (nausea, vomiting, weakness, pallor, perspiration and collapse/syncope) may occur even with therapeutic doses.

5.3 Hypertrophic Obstructive Cardiomyopathy

Nitrate therapy may aggravate the angina caused by hypertrophic cardiomyopathy.

5.4 Headache

Nitroglycerin produces dose-related headaches, especially at the start of nitroglycerin therapy, which may be severe and persist but usually subside with continued use.

6 ADVERSE REACTIONS

The following adverse reactions are discussed in more detail elsewhere in the label:

Hypotension [see Warnings and Precautions (5.2)]
Headache [see Warnings and Precautions (5.4)]
Hypersensitivity [see Contraindications (4.4)]

Vertigo, dizziness, weakness, palpitation, and other manifestations of postural hypotension may develop occasionally, particularly in erect, immobile patients. Marked sensitivity to the hypotensive effects of nitrates (manifested by nausea, vomiting, weakness, diaphoresis, pallor, and collapse) may occur at therapeutic doses. Syncope due to nitrate vasodilatation has been reported.

Flushing, drug rash, and exfoliative dermatitis have been reported in patients receiving nitrate therapy.

7 DRUG INTERACTIONS

Ergotamine: increased bioavailability of ergotamine. Avoid concomitant use. (7.2)

See 17 for PATIENT COUNSELING INFORMATION and FDA-approved patient labeling.

Revised: 10/2021

7.1 PDE-5-Inhibitors and sGC-Stimulators

Nitroglycerin sublingual tablets are contraindicated in patients who are using a selective inhibitor of cyclic guanosine monophosphate (cGMP)-specific phosphodiesterase type 5 (PDE-5). PDE-5-Inhibitors such as avanafil, sildenafil, vardenafil, and tadalafil have been shown to potentiate the hypotensive effects of organic nitrates.

Nitroglycerin sublingual tablets are contraindicated in patients who are taking soluble guanylate cyclase (sGC) stimulators. Concomitant use can cause hypotension.

The time course and dose dependence of these interactions have not been studied, and use within a few days of one another is not recommended. Appropriate supportive care for the severe hypotension has not been studied, but it seems reasonable to treat this as a nitrate overdose, with elevation of the extremities and with central volume expansion.

7.2 Ergotamine

Oral administration of nitroglycerin markedly decreases the first-pass metabolism of dihydroergotamine and subsequently increases its oral bioavailability. Ergotamine is known to precipitate angina pectoris. Therefore, patients receiving sublingual nitroglycerin should avoid ergotamine and related drugs or be monitored for symptoms of ergotism if this is not possible.

8 USE IN SPECIFIC POPULATIONS

8.1 Pregnancy

Risk Summary

Limited published data on the use of nitroglycerin are insufficient to determine a drug associated risk of major birth defects or miscarriage. In animal reproduction studies, there were no adverse developmental effects when nitroglycerin was administered intravenously to rabbits or intraperitoneally to rats during organogenesis at doses greater than 64-times the human dose [see Data].

The estimated background risk of major birth defects and miscarriage for the indicated population is unknown. In the U.S. general population, the estimated background risk of major birth defects and miscarriage in clinically recognized pregnancies is 2 to 4% and 15 to 20%, respectively.

Data

Animal Data

No embryotoxic or postnatal development effects were observed with transdermal application in pregnant rabbits and rats at doses up to 80 and 240 mg/kg/day, respectively, at intraperitoneal doses in pregnant rats up to 20 mg/kg/day from gestation day 7 to 17, and at intravenous doses in pregnant rabbits up to 4 mg/kg/day from gestation day 6 to 18.

8.2 Lactation

Risk Summary

Sublingual nitroglycerin has not been studied in lactating women. It is not known if nitroglycerin is present in human milk or if nitroglycerin has effects on milk production.

8.4 Pediatric Use

The safety and effectiveness of nitroglycerin in pediatric patients have not been established.

8.5 Geriatric Use

Clinical studies of nitroglycerin sublingual tablets did not include sufficient numbers of subjects aged 65 and over to determine whether they respond differently from younger subjects. Other reported clinical experience has not identified differences in responses between the elderly and younger patients. In general, dose selection for an elderly patient should be cautious, usually starting at the low end of the dosing range, reflecting the greater frequency of decreased hepatic, renal, or cardiac function, and of concomitant disease or other drug therapy.

10 OVERDOSAGE

10.1 Signs and Symptoms, Methemoglobinemia

Nitrate overdosage may result in: severe hypotension, persistent throbbing headache, vertigo, palpitation, visual disturbance, flushing and perspiring skin (later becoming cold and cyanotic), nausea and vomiting (possibly with colic and even bloody diarrhea), syncope (especially in the upright posture), methemoglobinemia with cyanosis and anorexia, initial hyperpnea, dyspnea and slow breathing, slow pulse (dicrotic and intermittent), heart block, increased intracranial pressure with cerebral symptoms of confusion and moderate fever, paralysis and coma followed by clonic convulsions, and possibly death due to circulatory collapse.

Case reports of clinically significant methemoglobinemia are rare at conventional doses of organic nitrates. The formation of methemoglobin is dose-related and in the case of genetic abnormalities of hemoglobin that favor methemoglobin formation, even conventional doses of organic nitrates could produce harmful concentrations of methemoglobin.

10.2 Treatment of Overdosage

As hypotension associated with nitroglycerin overdose is the result of venodilatation and arterial hypovolemia, prudent therapy in this situation should be directed toward increase in central fluid volume. No specific antagonist to the vasodilator effects of nitroglycerin is known. Keep the patient recumbent in a shock position and comfortably warm. Passive movement of the extremities may aid venous return. Intravenous infusion of normal saline or similar fluid may also be necessary. Administer oxygen and artificial ventilation, if necessary. If methemoglobinemia is present, administration of methylene blue (1% solution), 1 to 2 mg per kilogram of body weight intravenously, may be required unless the patient is known to have G-6-PD deficiency. If an excessive quantity of nitroglycerin has been recently swallowed gastric lavage may be of use.

As epinephrine is ineffective in reversing the severe hypotensive events associated with overdosage, it is not recommended for resuscitation.

11 DESCRIPTION

Nitroglycerin Sublingual Tablets, USP are stabilized sublingual compressed nitroglycerin tablet that contains 0.3 mg, 0.4 mg, or 0.6 mg nitroglycerin; as well as calcium stearate, croscarmellose sodium, silica dimethyl silylate and lactose monohydrate.

Nitroglycerin, an organic nitrate, is a vasodilating agent. The chemical name for nitroglycerin is 1, 2, 3 propanetriol trinitrate and the chemical structure is:

Molecular weight: 227.09 g/mol

12 CLINICAL PHARMACOLOGY

12.1 Mechanism of Action

Nitroglycerin forms free radical nitric oxide (NO) which activates guanylate cyclase, resulting in an increase of guanosine 3'5' monophosphate (cyclic GMP) in smooth muscle and other tissues. These events lead to dephosphorylation of myosin light chains, which regulate the contractile state in smooth muscle, and result in vasodilatation.

12.2 Pharmacodynamics

The principal pharmacological action of nitroglycerin is relaxation of vascular smooth muscle. Although venous effects predominate, nitroglycerin produces, in a dose-related manner, dilation of both arterial and venous beds. Dilation of postcapillary vessels, including large veins, promotes peripheral pooling of blood, decreases venous return to the heart, and reduces left ventricular end-diastolic pressure (preload).

Nitroglycerin also produces arteriolar relaxation, thereby reducing peripheral vascular resistance and arterial pressure (afterload), and dilates large epicardial coronary arteries; however, the extent to which this latter effect contributes to the relief of exertional angina is unclear.

Therapeutic doses of nitroglycerin may reduce systolic, diastolic, and mean arterial blood pressure. Effective coronary perfusion pressure is usually maintained, but can be compromised if blood pressure falls excessively, or increased heart rate decreases diastolic filling time.

Elevated central venous and pulmonary capillary wedge pressures, and pulmonary and systemic vascular resistance are also reduced by nitroglycerin therapy. Heart rate is usually slightly increased, presumably due to a compensatory response to the fall in blood pressure. Cardiac index may be increased, decreased, or unchanged. Myocardial oxygen consumption or demand (as measured by the pressure-rate product, tension-time index, and stroke-work index) is decreased and a more favorable supply-demand ratio can be achieved. Patients with elevated left ventricular filling pressures and increased systemic vascular resistance in association with a depressed cardiac index are likely to experience an improvement in cardiac index. In contrast, when filling pressures and cardiac index are normal, cardiac index may be slightly reduced following nitroglycerin administration.

Consistent with the symptomatic relief of angina, digital plethysmography indicates that onset of the vasodilatory effect occurs approximately 1 to 3 minutes after sublingual nitroglycerin administration and reaches a maximum by 5 minutes postdose. Effects persist for at least 25 minutes following nitroglycerin administration.

12.3 Pharmacokinetics

Absorption

Nitroglycerin is rapidly absorbed following sublingual administration of nitroglycerin sublingual tablets. Mean peak nitroglycerin plasma concentrations occur at a mean time of approximately 6 to 7 minutes postdose (Table 1). Maximum plasma nitroglycerin concentrations (Cmax) and area under the plasma concentration-time curves (AUC) increase dose-proportionally following 0.3 to 0.6 mg nitroglycerin. The absolute bioavailability of nitroglycerin from nitroglycerin sublingual tablets is approximately 40% but tends to be variable due to factors influencing drug absorption, such as sublingual hydration and mucosal metabolism.

Table 1
 | Mean Nitroglycerin (SD) Values
 | 2 x 0.3 mg | 1 x 0.6 mg
Parameter | Nitroglycerin Sublingual Tablets | Nitroglycerin Sublingual Tablets
Cmax, ng/mL | 2.3 (1.7) | 2.1 (1.5)
Tmax, min | 6.4 (2.5) | 7.2 (3.2)
AUC (0-∞), min | 14.9 (8.2) | 14.9 (11.4)
t½, min | 2.8 (1.1) | 2.6 (0.6)

Distribution

The volume of distribution (VArea) of nitroglycerin following intravenous administration is 3.3 L/kg. At plasma concentrations between 50 and 500 ng/mL, the binding of nitroglycerin to plasma proteins is approximately 60%, while that of 1,2- and 1,3-dinitroglycerin is 60% and 30%, respectively.

Metabolism

A liver reductase enzyme is of primary importance in the metabolism of nitroglycerin to glycerol di- and mononitrate metabolites and ultimately to glycerol and organic nitrate. Known sites of extrahepatic metabolism include red blood cells and vascular walls. In addition to nitroglycerin, 2 major metabolites 1,2- and 1,3-dinitroglycerin, are found in plasma. Mean peak 1,2- and 1,3-dinitroglycerin plasma concentrations occur at approximately 15 minutes postdose. The elimination half-life of 1,2- and 1,3-dinitroglycerin is 36 and 32 minutes, respectively. The 1,2- and 1,3-dinitroglycerin metabolites have been reported to possess approximately 2% and 10%, respectively, of the pharmacological activity of nitroglycerin. Higher plasma concentrations of the dinitro metabolites, along with their nearly 10-fold longer elimination half-lives, may contribute significantly to the duration of pharmacologic effect. Glycerol mononitrate metabolites of nitroglycerin are biologically inactive.

Elimination

Nitroglycerin plasma concentrations decrease rapidly, with a mean elimination half-life of 2 to 3 minutes. Half-life values range from 1.5 to 7.5 minutes. Clearance (13.6 L/min) greatly exceeds hepatic blood flow. Metabolism is the primary route of drug elimination.

Drug interactions

Aspirin: Coadministration of nitroglycerin with high dose aspirin (1000 mg) results in increased exposure to nitroglycerin. The vasodilatory and hemodynamic effects of nitroglycerin may be enhanced by concomitant administration of nitroglycerin with high dose aspirin.

Tissue-type plasminogen activator (t-PA): Concomitant administration of t-PA and intravenous nitroglycerin has been shown to reduce plasma levels of t-PA and its thrombolytic effect.

13 NONCLINICAL TOXICOLOGY

13.1 Carcinogenesis, Mutagenesis, Impairment of Fertility

Animal carcinogenesis studies with sublingually administered nitroglycerin have not been performed.

Carcinogenicity potential of nitroglycerin was evaluated in rats receiving up to 434 mg/kg/day of dietary nitroglycerin for 2 years. Rats developed dose-related fibrotic and neoplastic changes in liver, including carcinomas, and interstitial cell tumors in testes. At high dose, the incidences of hepatocellular carcinomas in males was 48% and in females was 33%, compared to 0% in untreated controls. Incidences of testicular tumors were 52% vs. 8% in controls. Lifetime dietary administration of up to 1058 mg/kg/day of nitroglycerin was not tumorigenic in mice.

Nitroglycerin was mutagenic in Ames tests performed in 2 different laboratories. Nevertheless, there was no evidence of mutagenicity in an in vivo dominant lethal assay with male rats treated with doses up to about 363 mg/kg/day, PO, or in ex vivo cytogenetic tests in rat and dog cells.

In a 3-generation reproduction study, rats received dietary nitroglycerin at doses up to about 434 mg/kg/day for 6 months prior to mating of the F0 generation, with treatment continuing through successive F1 and F2 generations. The high dose was associated with decreased feed intake and body weight gain in both sexes at all matings. No specific effect on the fertility of the F0 generation was seen. Infertility noted in subsequent generations, however, was attributed to increased interstitial cell tissue and aspermatogenesis in the high-dose males. In this 3-generation study, there was no clear evidence of teratogenicity.

16 HOW SUPPLIED/STORAGE AND HANDLING

Nitroglycerin Sublingual Tablets, USP are supplied as white to off white, round, flat-faced tablets in 3 strengths (0.3 mg, 0.4 mg, and 0.6 mg) in bottles.

Store at 20°C to 25°C (68°F to 77°F) [see USP Controlled Room Temperature]. Nitroglycerin should be kept in the original glass container and must be tightly capped after each use to prevent loss of tablet potency.

17 PATIENT COUNSELING INFORMATION

Advise the patient to read the FDA-approved patient labeling (Patient Information).

This product's label may have been updated. For full prescribing information, please visit www.glenmarkpharma-us.com.

Manufactured by:

Glenmark Pharmaceuticals Limited

India

Manufactured for:

Glenmark Pharmaceuticals Inc., USA

Mahwah, NJ 07430

Questions? 1 (888) 721-7115

www.glenmarkpharma-us.com

October 2021

Patient Information

Nitroglycerin (nahy-truh-glis-er-in)
Sublingual Tablets, USP

Read this information carefully before you start nitroglycerin sublingual tablets and each time you refill your prescription. There may be new information. This information does not replace talking with your doctor. If you have any questions about nitroglycerin sublingual tablets, ask your doctor. Your doctor will know if nitroglycerin sublingual tablets are right for you.

What are Nitroglycerin Sublingual Tablets?

Nitroglycerin sublingual tablets are type of medicine known as an organic nitrate and is a vasodilating agent. It is used to treat a type of chest pain called angina.

What is Angina?

Angina is a pain or discomfort that keeps coming back when part of your heart does not get enough blood. Angina feels like a pressing or squeezing pain, usually in your chest under the breastbone. Sometimes you can feel it in your shoulders, arms, neck, jaws, or back. Nitroglycerin sublingual tablets can relieve this pain.

Who should not use Nitroglycerin Sublingual Tablets?

Do not use nitroglycerin sublingual tablets if you are allergic to organic nitrates (like the active ingredient in nitroglycerin).

You should not take nitroglycerin sublingual tablets if you have the following conditions:

- very recent heart attack
- severe anemia
- increased pressure in the head

Do not take nitroglycerin sublingual tablets with drugs for erectile dysfunction, like VIAGRA® (sildenafil citrate), CIALIS® (tadalafil), or LEVITRA® (vardenafil hydrochloride), as this may lead to extreme lowering of your blood pressure.

Do not take nitroglycerin sublingual tablets if you take medicines called guanylate cyclase stimulators which include riociguat, a medicine that treats pulmonary arterial hypertension and chronic-thromboembolic pulmonary hypertension.

What should I tell my doctor before taking Nitroglycerin Sublingual Tablets?

Before using nitroglycerin sublingual tablets, tell your doctor if:

- You are taking any medicines that are used to treat angina, heart failure, or an irregular heartbeat.
- You are taking any medicines that reduce blood pressure.
- You are taking any diuretics (water pills).
- You are taking medicines that can cause dry mouth such as tricyclic antidepressants (e.g. amitriptyline, desipramine, doxepin), anticholinergic drugs, or any antimuscarinic drugs (e.g. atropine).
- You are taking ergotamine or similar drugs for migraine headaches.
- You are taking aspirin.
- You are taking any medicines for erectile dysfunction.
- You are pregnant or plan to become pregnant.
- You are breastfeeding.

How should I take Nitroglycerin Sublingual Tablets?

- Do not chew, crush, or swallow nitroglycerin sublingual tablets.
- You should sit down when taking nitroglycerin sublingual tablets and use caution when you stand up. This eliminates the possibility of falling due to lightheadedness or dizziness.
- One tablet should be dissolved under the tongue or in the oral cavity at the first sign of chest pain.
- The dose may be repeated approximately every 5 minutes, until the chest pain is relieved.
- If the pain persists after a total of 3 tablets in a 15-minute period, or is different than you typically experience, call your doctor or seek emergency help.
- Nitroglycerin sublingual tablets may be used 5 to 10 minutes prior to activities that might cause chest pain.
- You may feel a burning or tingling sensation in your mouth when you take nitroglycerin sublingual tablets.

What should I avoid while taking Nitroglycerin Sublingual Tablets?

- Do not breastfeed. It is not known if nitroglycerin will pass through your milk.
- Do not consume alcohol while taking nitroglycerin sublingual tablets, as this can lower your blood pressure.
- Do not start any new prescription or non-prescription medicines or supplements, unless you check with your doctor first.

What are the possible side effects of Nitroglycerin Sublingual Tablets?

Nitroglycerin sublingual tablets may cause the following side effects:

- headache
- vertigo (a major symptom of balance disorder)
- dizziness
- weakness
- heart palpitations (unusual awareness of the heartbeat)
- low blood pressure upon rising from a seated position
- nausea and vomiting
- sweating
- paleness
- fainting
- flushing (warm or red condition of your skin)
- other skin reactions that may be severe

Tell your doctor if you are concerned about any side effects you experience. These are not all the possible side effects of nitroglycerin sublingual tablets. For a complete list, ask your doctor or pharmacist.

How do I store Nitroglycerin Sublingual Tablets?

Nitroglycerin sublingual tablets should be kept in the original glass container and tightly capped after each use to prevent loss of tablet potency.

Store nitroglycerin sublingual tablets at 20°C to 25°C (68°F to 77°F) [see USP Controlled Room Temperature].

General advice about Nitroglycerin Sublingual Tablets

Sometimes doctors will prescribe a medicine for a condition that is not included in the patient information leaflets. Only use nitroglycerin sublingual tablets the way your doctor told you to. Do not give nitroglycerin sublingual tablets to other people, even if they have the same symptoms you have. They may harm them.

You can ask your pharmacist or doctor for information about nitroglycerin sublingual tablets, or you can call Glenmark Pharmaceuticals Inc., USA at 1 (888) 721-7115.

Trademarks are the property of their respective owners.

Manufactured by:

Glenmark Pharmaceuticals Limited

India

Manufactured for:

Glenmark Pharmaceuticals Inc., USA

Mahwah, NJ 07430

Questions? 1 (888) 721-7115

www.glenmarkpharma-us.com

October 2021

DIPHENHYDRAMINE HYDROCHLORIDE INJECTION, USP

Rx only

DESCRIPTION

Diphenhydramine Hydrochloride Injection is a sterile, nonpyrogenic solution for intravenous or deep intramuscular use as an antihistaminic agent. Each mL contains diphenhydramine hydrochloride 50 mg and benzethonium chloride 100 mcg in Water for Injection. pH 4.0-6.5; sodium hydroxide and/or hydrochloric acid added, if needed, for pH adjustment.

The chemical name of diphenhydramine hydrochloride is 2-(Diphenylmethoxy)-N,N-dimethylethylamine hydrochloride. The structural formula is as follows:

C17H21NO • HCl MW 291.82

Diphenhydramine hydrochloride occurs as a white crystalline powder and is freely soluble in water and alcohol.

CLINICAL PHARMACOLOGY

Diphenhydramine hydrochloride is an antihistamine with anticholinergic (drying) and sedative side effects. Antihistamines appear to compete with histamine for cell receptor sites on effector cells.

Diphenhydramine hydrochloride in the injectable form has a rapid onset of action. Diphenhydramine is widely distributed throughout the body, including the CNS. A portion of the drug is excreted unchanged in the urine, while the rest is metabolized via the liver. Detailed information on the pharmacokinetics of Diphenhydramine Hydrochloride Injection is not available.

INDICATIONS AND USAGE

Diphenhydramine Hydrochloride Injection is effective in adults and pediatric patients, other than premature infants and neonates, for the following conditions when the oral form is impractical:

Antihistaminic

For amelioration of allergic reactions to blood or plasma, in anaphylaxis as an adjunct to epinephrine and other standard measures after the acute symptoms have been controlled and for other uncomplicated allergic conditions of the immediate type when oral therapy is impossible or contraindicated.

Motion Sickness

For active treatment of motion sickness.

Antiparkinsonism

For use in parkinsonism, when oral therapy is impossible or contraindicated, as follows: parkinsonism in the elderly who are unable to tolerate more potent agents, mild cases of parkinsonism in other age groups and in other cases of parkinsonism in combination with centrally acting anticholinergic agents.

CONTRAINDICATIONS

Use in Neonates or Premature Infants

This drug should not be used in neonates or premature infants.

Use in Nursing Mothers

Because of the higher risk of antihistamines for infants generally, and for neonates and prematures in particular, antihistamine therapy is contraindicated in nursing mothers.

Use as a Local Anesthetic

Because of the risk of local necrosis, this drug should not be used as a local anesthetic.

Antihistamines are also Contraindicated in the Following Conditions

Hypersensitivity to diphenhydramine hydrochloride and other antihistamines of similar chemical structure.

WARNINGS

Antihistamines should be used with considerable caution in patients with narrow-angle glaucoma, stenosing peptic ulcer, pyloroduodenal obstruction, symptomatic prostatic hypertrophy or bladder-neck obstruction.

Local necrosis has been associated with the use of subcutaneous or intradermal use of intravenous diphenhydramine.

Use in Pediatric Patients

In pediatric patients, especially, antihistamines in overdosage may cause hallucinations, convulsions or death.

As in adults, antihistamines may diminish mental alertness in pediatric patients. In the young pediatric patient, particularly, they may produce excitation.

Use in the Elderly (approximately 60 years or older)

Antihistamines are more likely to cause dizziness, sedation and hypotension in elderly patients.

PRECAUTIONS

General

Diphenhydramine hydrochloride has an atropine-like action and, therefore, should be used with caution in patients with a history of bronchial asthma, increased intraocular pressure, hyperthyroidism, cardiovascular disease or hypertension. Use with caution in patients with lower respiratory disease, including asthma.

Information for Patients

Patients taking diphenhydramine hydrochloride should be advised that this drug may cause drowsiness and has an additive effect with alcohol.

Patients should be warned about engaging in activities requiring mental alertness, such as driving a car or operating appliances, machinery, etc.

Drug Interactions

Diphenhydramine hydrochloride has additive effects with alcohol and other CNS depressants (hypnotics, sedatives, tranquilizers, etc.)

MAO inhibitors prolong and intensify the anticholinergic (drying) effects of antihistamines.

Carcinogenesis, Mutagenesis, Impairment of Fertility

Long-term studies in animals to determine mutagenic and carcinogenic potential have not been performed.

Pregnancy

Teratogenic Effects—Pregnancy Category B

Reproduction studies have been performed in rats and rabbits at doses up to 5 times the human dose and have revealed no evidence of impaired fertility or harm to the fetus due to diphenhydramine hydrochloride. There are, however, no adequate and well-controlled studies in pregnant women. Because animal reproduction studies are not always predictive of human response, this drug should be used during pregnancy only if clearly needed.

Pediatric Use

Diphenhydramine should not be used in neonates and premature infants (see CONTRAINDICATIONS).

Diphenhydramine may diminish mental alertness, or in the young pediatric patient, cause excitation. Overdosage may cause hallucinations, convulsions or death (see WARNINGS and OVERDOSAGE).

See also DOSAGE AND ADMINISTRATION section.

ADVERSE REACTIONS

The most frequent adverse reactions are italicized.

General

Urticaria; drug rash; anaphylactic shock; photosensitivity; excessive perspiration; chills; dryness of mouth, nose and throat.

Cardiovascular System

Hypotension, headache, palpitations, tachycardia, extrasystoles.

Hematologic System

Hemolytic anemia, thrombocytopenia, agranulocytosis.

Nervous System

Sedation, sleepiness, dizziness, disturbed coordination, fatigue, confusion, restlessness, excitation, nervousness, tremor, irritability, insomnia, euphoria, paresthesia, blurred vision, diplopia, vertigo, tinnitus, acute labyrinthitis, neuritis, convulsions.

Gastrointestinal System

Epigastric distress, anorexia, nausea, vomiting, diarrhea, constipation.

Genitourinary System

Urinary frequency, difficult urination, urinary retention, early menses.

Respiratory System

Thickening of bronchial secretions, tightness of chest and wheezing, nasal stuffiness.

OVERDOSAGE

Antihistamine overdosage reactions may vary from central nervous system depression to stimulation. Stimulation is particularly likely in pediatric patients. Atropine-like signs and symptoms, dry mouth; fixed, dilated pupils; flushing, and gastrointestinal symptoms may also occur.

Stimulants should not be used.

Vasopressors may be used to treat hypotension.

DOSAGE AND ADMINISTRATION

THIS PRODUCT IS FOR INTRAVENOUS OR INTRAMUSCULAR ADMINISTRATION ONLY.

Diphenhydramine Hydrochloride Injection is indicated when the oral form is impractical.

DOSAGE SHOULD BE INDIVIDUALIZED ACCORDING TO THE NEEDS AND THE RESPONSE OF THE PATIENT.

Pediatric Patients, Other Than Premature Infants and Neonates

5 mg/kg/24 hours or 150 mg/m^2/24 hours. Maximum daily dosage is 300 mg. Divide into four doses, administered intravenously at a rate generally not exceeding 25 mg/min, or deep intramuscularly.

Adults

10 to 50 mg intravenously at a rate generally not exceeding 25 mg/min, or deep intramuscularly; 100 mg if required; maximum daily dosage is 400 mg.

Parenteral drug products should be inspected visually for particulate matter and discoloration prior to administration, whenever solution and container permit.

HOW SUPPLIED

Diphenhydramine Hydrochloride Injection, USP 50 mg/mL

Storage

Protect from light. Keep covered in carton until time of use. Store at 20° to 25°C (68° to 77°F), excursions permitted to 15° to 30°C (59° to 86°F) [See USP Controlled Room Temperature].

To report SUSPECTED ADVERSE REACTIONS, contact Hikma Pharmaceuticals USA Inc. at 1-877-845-0689, or the FDA at 1-800-FDA-1088 or www.fda.gov/medwatch.
For Product Inquiry call 1-877-845-0689.

Manufactured by:
Hikma Pharmaceuticals USA Inc.
Berkeley Heights, NJ 07922

Revised December 2019

BAYER GENUINE ASPIRIN TABLETS

Drug Facts

Active ingredient (in each tablet)

Aspirin 325 mg (NSAID)^1

^1nonsteroidal anti-inflammatory drug

Purposes

Pain reliever/fever reducer

Uses

- temporarily relieves minor aches and pains due to:
- headache
- muscle pain
- toothache
- menstrual pain
- colds
- minor pain of arthritis

- temporarily reduces fever

Warnings

Reye's syndrome:
Children and teenagers who have or are recovering from chicken pox or flu-like symptoms should not use this product. When using this product, if changes in behavior with nausea and vomiting occur, consult a doctor because these symptoms could be an early sign of Reye's syndrome, a rare but serious illness.

Allergy alert:
Aspirin may cause a severe allergic reaction which may include:

- hives
- facial swelling
- asthma (wheezing)
- shock

Stomach bleeding warning:
This product contains an NSAID, which may cause severe stomach bleeding. The chance is higher if you

- are age 60 or older
- have had stomach ulcers or bleeding problems
- take a blood thinning (anticoagulant) or steroid drug
- take other drugs containing prescription or nonprescription NSAIDs (aspirin, ibuprofen, naproxen, or others)
- have 3 or more alcoholic drinks every day while using this product
- take more or for a longer time than directed

Do not use

- if you are allergic to aspirin or any other pain reliever/fever reducer
- if you have ever had an allergic reaction to this product or any of its ingredients

Ask a doctor before use if

- stomach bleeding warning applies to you
- you have a history of stomach problems, such as heartburn
- you have high blood pressure, heart disease, liver cirrhosis, or kidney disease
- you are taking a diuretic
- you have asthma

Ask a doctor or pharmacist before use if you are taking a prescription drug for

- gout
- diabetes
- arthritis

Stop use and ask doctor if

- an allergic reaction occurs. Seek medical help right away.
- you experience any of the following signs of stomach bleeding:
- feel faint
- vomit blood
- have bloody or black stools
- have stomach pain that does not get better

- pain gets worse or lasts more than 10 days
- fever gets worse or lasts more than 3 days
- redness or swelling is present
- new symptoms occur
- ringing in the ears or a loss of hearing occurs

If pregnant or breast-feeding, ask a health professional before use.

It is especially important not to use aspirin during the last 3 months of pregnancy unless definitely directed to do so by a doctor because it may cause problems in the unborn child or complications during delivery.

Keep out of reach of children. In case of overdose, get medical help or contact a Poison Control Center right away.

Directions

- drink a full glass of water with each dose
- adults and children 12 years and over: take 1 or 2 tablets every 4 hours or 3 tablets every 6 hours, not to exceed 12 tablets in 24 hours
- children under 12 years: consult a doctor

Other information

- save carton for full directions and warnings
- store at room temperature

Inactive ingredients

corn starch, hypromellose, powdered cellulose, triacetin

Questions?

1-800-331-4536 (Mon-Fri 9AM-5PM EST)

This product is repackaged by: Select Corporation
1433 Wainwright Way, Carrollton, TX 75007
877-244-4400 M - F 9am - 5 pm, from a product manufactured by Bayer.

Dist. by: Bayer HealthCare LLC
Whippany, NJ 07981

GOOD SENSE ALLERGY - DIPHENHYDRAMINE HCl SOLUTION

Drug Facts

Active ingredient (in each 5 mL)

Diphenhydramine HCl 12.5 mg

Purpose

Antihistamine

Uses

- temporarily relieves these symptoms due to hay fever or other upper respiratory allergies:
- sneezing
- itching of the nose or throat
- runny nose
- itchy, watery eyes

Warnings

Do not use

- with any other product containing diphenhydramine, even one used on skin
- to make a child sleepy

Ask a doctor before use if the child has

- a breathing problem such as chronic bronchitis
- glaucoma
- a sodium-restricted diet

Ask a doctor or pharmacist before use if the child is taking sedatives or tranquilizers

When using this product

- marked drowsiness may occur
- excitability may occur, especially in children
- sedatives and tranquilizers may increase drowsiness

Keep out of reach of children. In case of overdose, get medical help or contact a Poison Control Center right away (1-800-222-1222).

Directions

- find right dose on chart below
- mL = milliliter
- take every 4 to 6 hours, or as directed by a doctor
- do not take more than 6 doses in 24 hours

Age (yr) | Dose (mL)
children under 2 years | do not use
children 2 to 5 years | do not use unless directed by a doctor
children 6 to 11 years | 5 mL to 10 mL

Attention: use only enclosed dosing cup specifically designed for use with this product. Do not use any other dosing device.

Other Information

- each 5 mL contains: sodium 15 mg
- store at 20-25°C (68-77°F). Protect from light. Store in outer carton until contents used.
- do not use if printed neckband is broken or missing

Inactive Ingredients

anhydrous citric acid, D&C red #33, FD&C red #40, flavor, glycerin, high fructose corn syrup, poloxamer 407, purified water, sodium benzoate, sodium chloride, sodium citrate, sorbitol solution

Questions or comments?

1-800-719-9260

Compared to active ingredient of Children's Benadryl® Allergy Liquid

Distributed By Perrigo®

Allegan, MI 49010

TRUEplus GLUCOSE TABLETS

15 g Fast acting Carbohydrates per Serving

Raises low blood sugar and boosts energy

Fat Free
Gluten Free
Sodium Free

ORANGE NATURALLY & ARTIFICIALLY FLAVORED

DO NOT USE IF PROTECTIVE SEAL IS BROKEN OR MISSING

QUESTIONS? Call 1-800-803-6025

INGREDIENTS: DEXTROSE (D-GLUCOSE), MALTODEXTRIN, CITRIC ACID, MAGNESIUM STEARATE, MICROCRYSTALLINE CELLUOSE, NATURAL & ARTIFICIAL ORANGE FLAVOR, ASCORBIC ACID, YELLOW #6.

DIRECTIONS

Chew desired amount of glucose.

Store at room temperature. Do not refrigerate or freeze. Do not expose to excessive heat or moisture.

Distributed by McKesson
6555, State Highway 161,
Las Colinas, TX 75039

TRUEplus is a trademark of Trivida Health, Inc.

healthmart.com

KIT CONTAINS:

EPINEPHRINE AUTO-INJECT (0.3 mg) – 1 no.
EPINEPHRINE AUTO-INJECT (0.15 mg) – 1 no.
ALBUTEROL SULFATE HFA INHALER (90 mcg) – 1 no.
NITROGLYCERIN SUBLINGUAL TABLETS (0.4 mg) – 1 bottle (25 tablets)
DIPHENHYDRAMINE HCl INJECTION SOLUTION (50 mg/mL) – 1 vial
ASPIRIN TABLETS (325 mg) – 1 Pouch (2 nos).
DIPHENHYDRAMINE HCl ORAL SOLUTION (118 mL) – 1 bottle
GLUCOSE TABLETS – 1 bottle (10 nos).
BD PLASTIPAK 3 mL SYRINGE 25GX1-1/2" – 1 no.

BESTDENTAL.COM